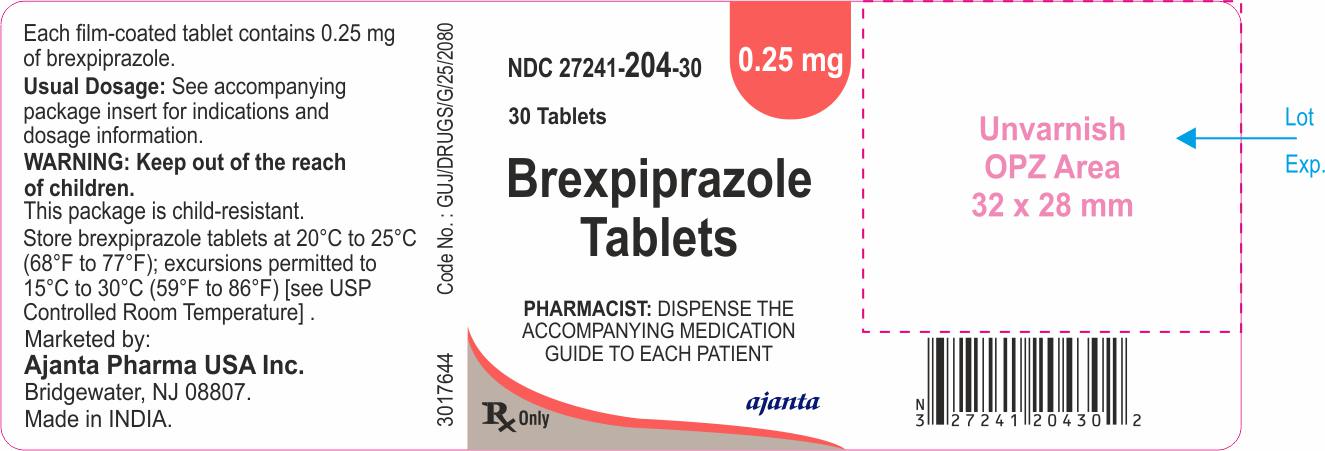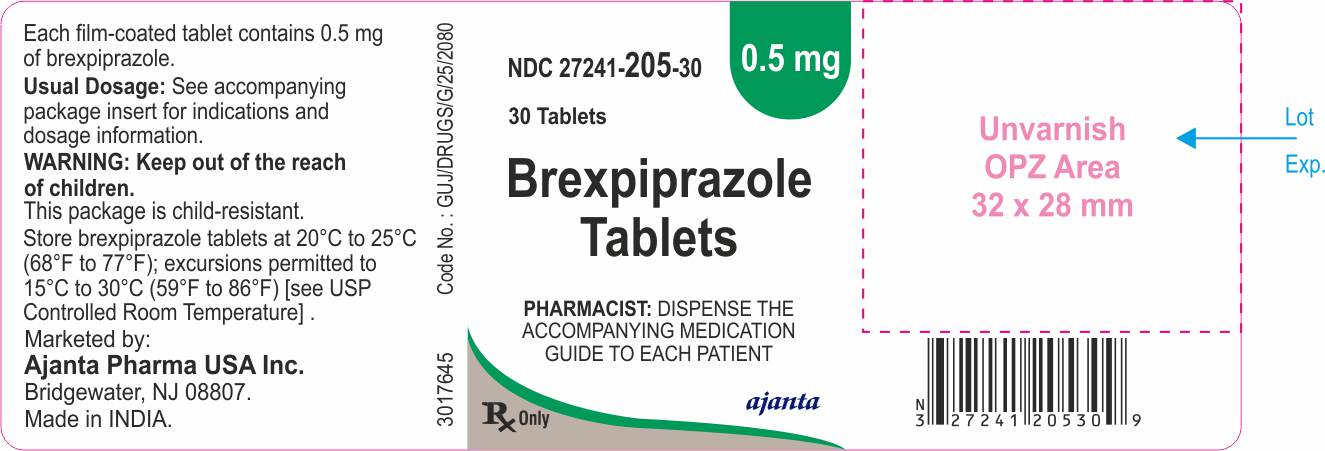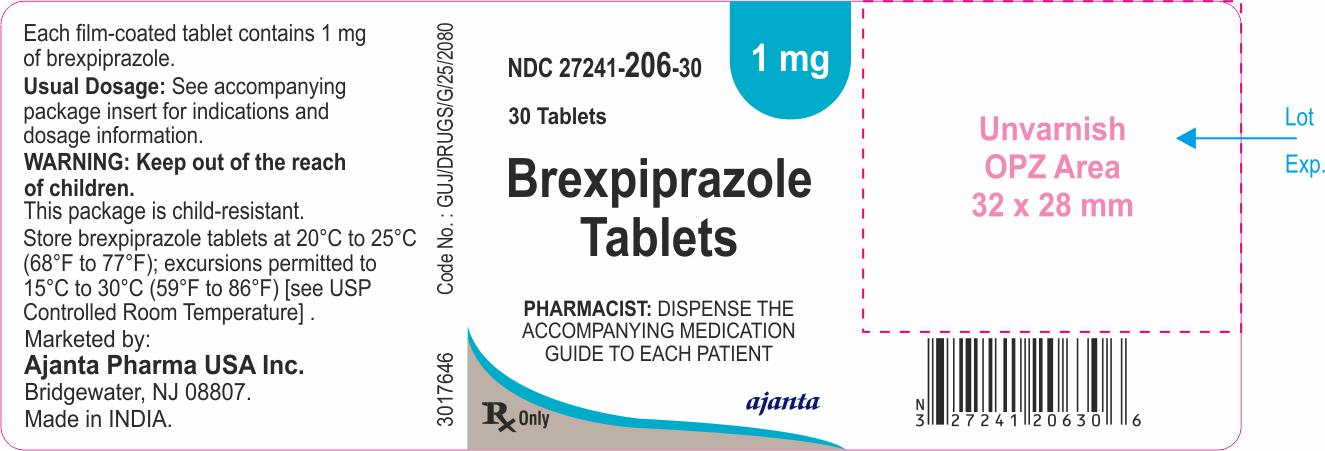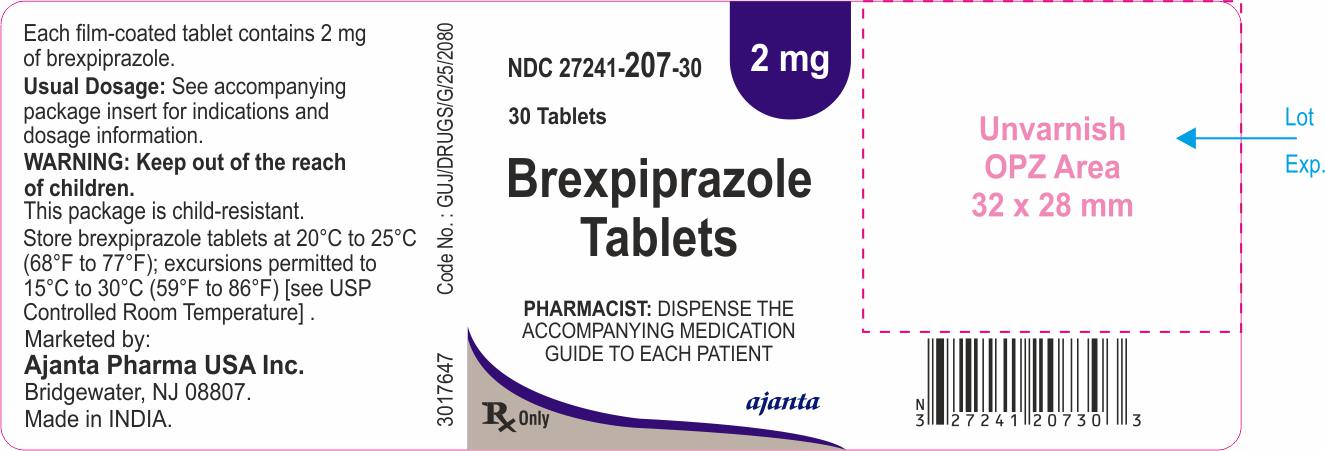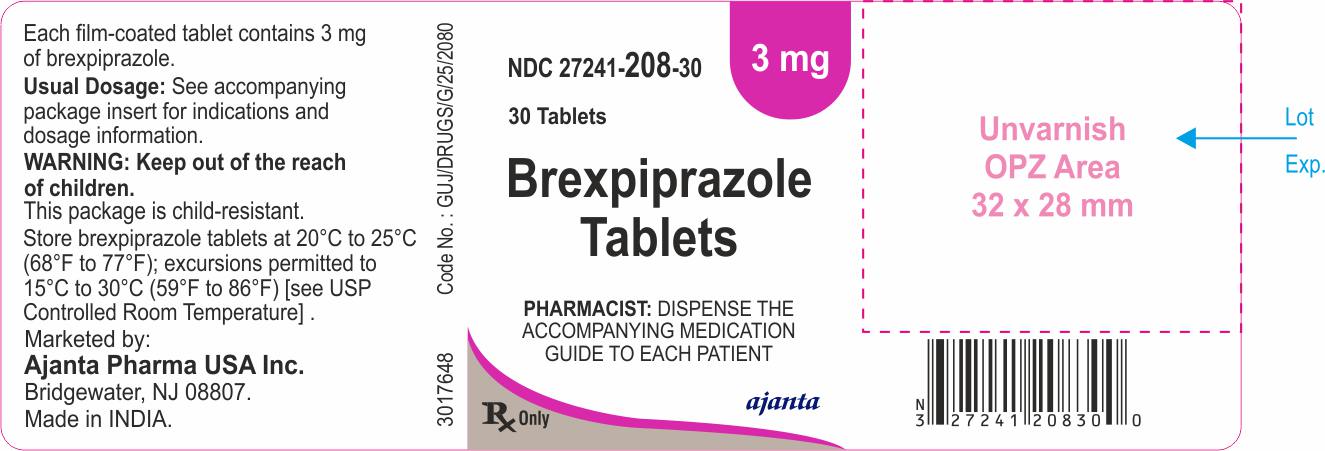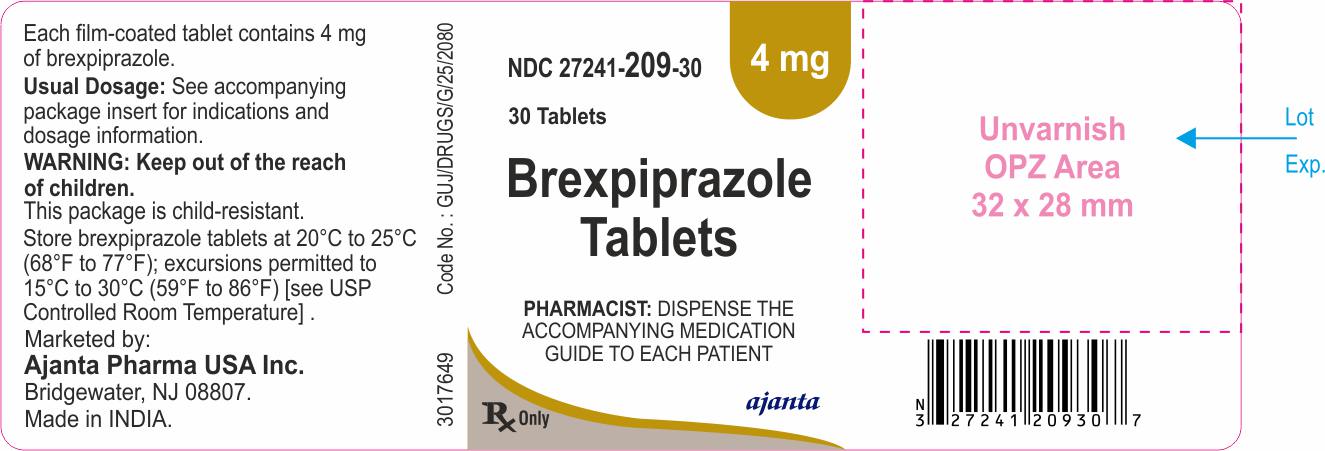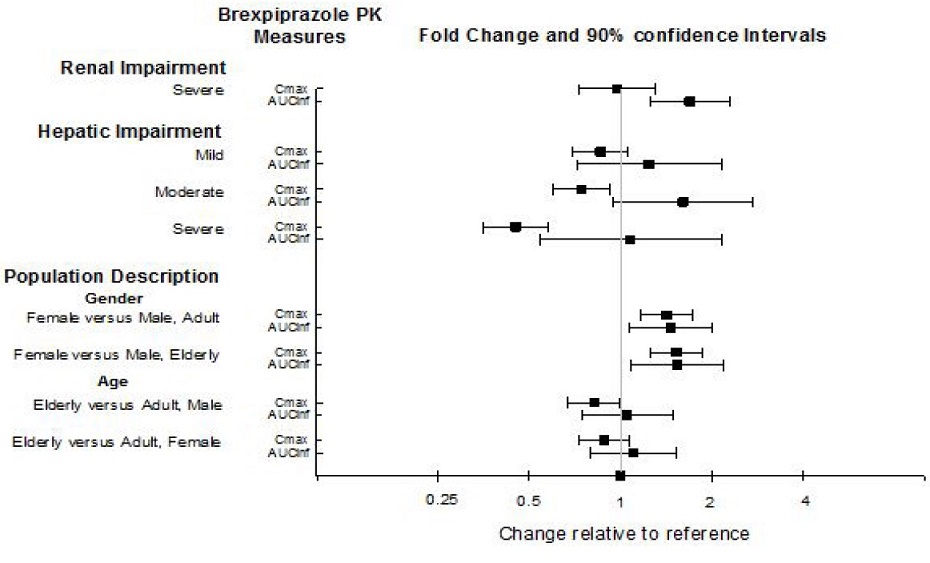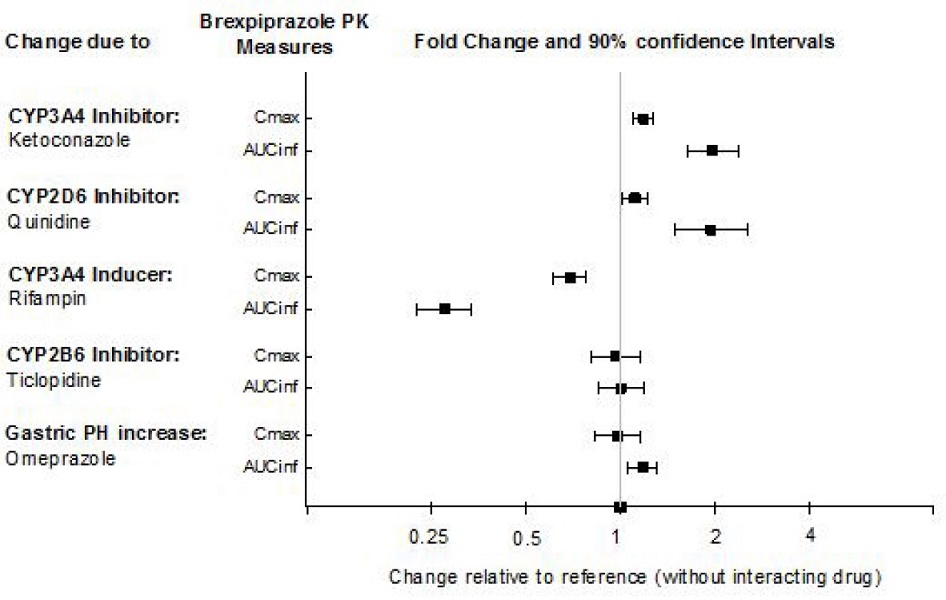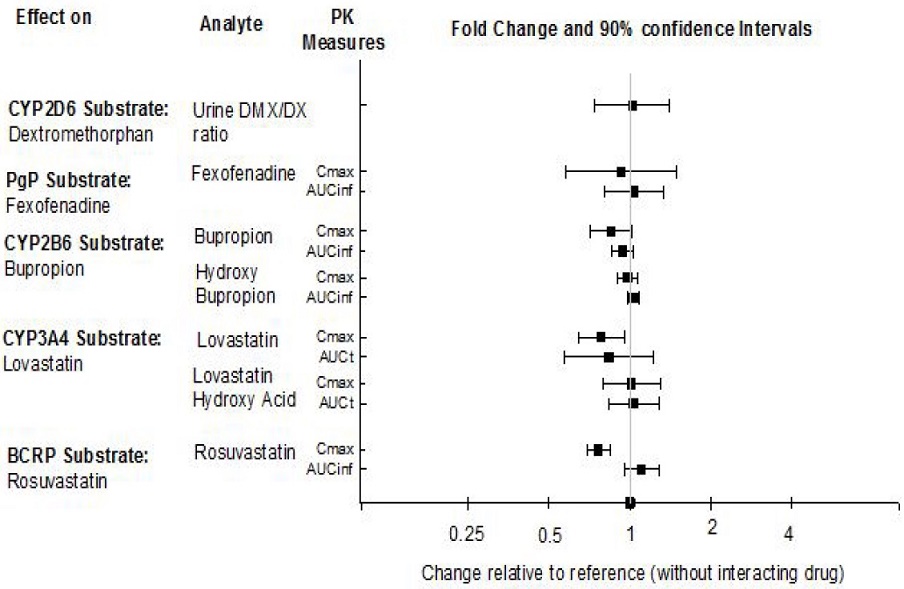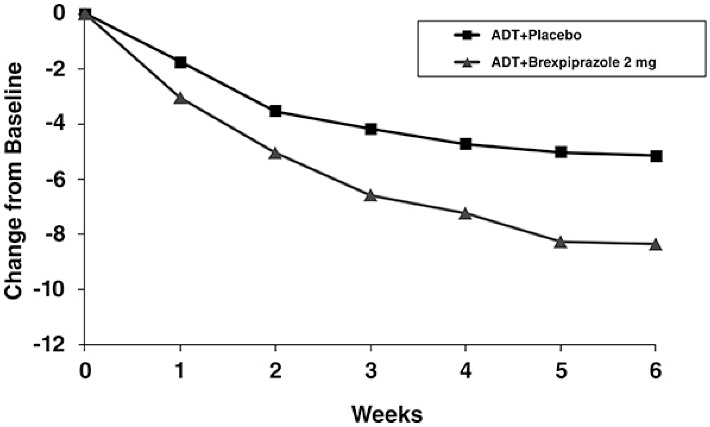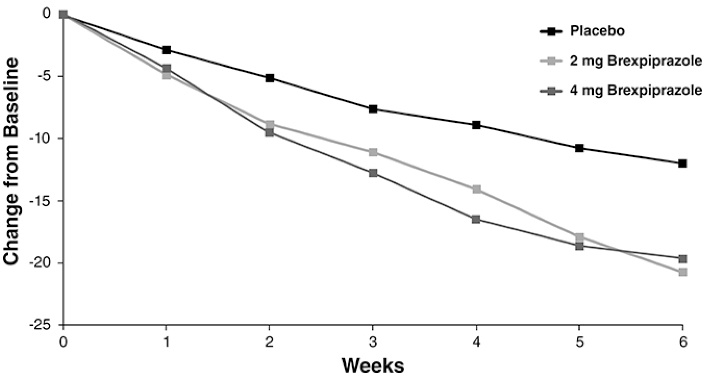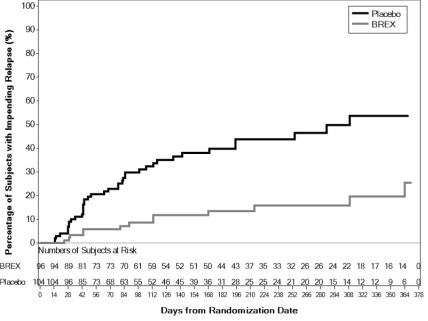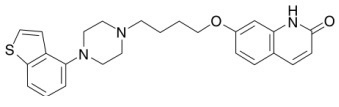 DRUG LABEL: Brexpiprazole
NDC: 27241-204 | Form: TABLET
Manufacturer: Ajanta Pharma USA Inc.
Category: prescription | Type: Human Prescription Drug Label
Date: 20221213

ACTIVE INGREDIENTS: BREXPIPRAZOLE 0.25 mg/1 1
INACTIVE INGREDIENTS: LACTOSE MONOHYDRATE; MICROCRYSTALLINE CELLULOSE; HYDROXYPROPYL CELLULOSE, UNSPECIFIED; LOW-SUBSTITUTED HYDROXYPROPYL CELLULOSE, UNSPECIFIED; MAGNESIUM STEARATE; HYPROMELLOSE, UNSPECIFIED; TALC; TITANIUM DIOXIDE; PROPYLENE GLYCOL; FERRIC OXIDE RED

HIGHLIGHTS OF PRESCRIBING INFORMATION

These highlights do not include all the information needed to use BREXPIPRAZOLE TABLETS safely and effectively. See full prescribing information for BREXPIPRAZOLE TABLETS.
BREXPIPRAZOLE tablets, for oral use
Initial U.S. Approval: 2015

RECENT MAJOR CHANGES

Boxed Warning 12/2021
Warnings and Precautions (5.6) 12/2021

WARNING: INCREASED MORTALITY IN ELDERLY PATIENTS WITH DEMENTIA-RELATED PSYCHOSIS and SUICIDAL THOUGHTS AND BEHAVIORS

See full prescribing information for complete boxed warning.

- Elderly patients with dementia-related psychosis treated with antipsychotic drugs are at increased risk of death. Brexpiprazole tablets are not approved for the treatment of patients with dementia-related psychosis. (5.1)
- Antidepressants increased the risk of suicidal thoughts and behaviors in patients aged 24 years and younger. Monitor for clinical worsening and emergence of suicidal thoughts and behaviors. Safety and effectiveness of brexpiprazole tablets have not been established in pediatric patients with MDD. (5.2, 8.4)

1 INDICATIONS AND USAGE

Brexpiprazole tablets is an atypical antipsychotic indicated for:

- Use as an adjunctive therapy to antidepressants for the treatment of major depressive disorder (MDD) in adults (1, 14.1)
- Treatment of schizophrenia in adults

2 DOSAGE AND ADMINISTRATION

Administer brexpiprazole tabletsonce daily with or without food. (2.1,2.2,12.3)

Indication | Starting Dose | Recommended Dose | Maximum Dose
MDD Adults (2.1) | 0.5 mg/day or 1 mg/day | 2 mg/day | 3 mg/day
Schizophrenia Adults (2.2) | 1 mg/day | 2 to 4 mg/day | 4 mg/day

- Moderate to Severe Hepatic Impairment (Child-Pugh score greater than or equal to 7): Maximum recommended dosage is 2 mg once daily for patients with MDD and 3 mg once daily for patients with schizophrenia. (2.3)
- Moderate, Severe or End-Stage Renal Impairment (CrCl less than 60 mL/minute): Maximum recommended dosage is 2 mg once daily for patients with MDD and 3 mg once daily for patients with schizophrenia. (2.4)
- Known CYP2D6 Poor Metabolizers: Reduce the usual dosage by half. (2.5)

3 DOSAGE FORMS AND STRENGTHS

Tablets: 0.25 mg, 0.5 mg, 1 mg, 2 mg, 3 mg, and 4 mg (3)

4 CONTRAINDICATIONS

Known hypersensitivity to brexpiprazole tablets or any of its components (4)

5 WARNINGS AND PRECAUTIONS

- Cerebrovascular Adverse Reactions in Elderly Patients with Dementia-Related Psychosis: Increased incidence of cerebrovascular adverse reactions (e.g., stroke, transient ischemic attack). (5.3)
- Neuroleptic Malignant Syndrome: Manage with immediate discontinuation and close monitoring. (5.4)
- Tardive Dyskinesia: Discontinue if clinically appropriate. (5.5)
- Metabolic Changes: Monitor for hyperglycemia/diabetes mellitus, dyslipidemia and weight gain. (5.6)
- Pathological Gambling and Other Compulsive Behaviors: Consider dose reduction or discontinuation. (5.7)
- Leukopenia, Neutropenia, and Agranulocytosis: Perform complete blood counts (CBC) in patients with pre-existing low white blood cell count (WBC) or history of leukopenia or neutropenia. Consider discontinuing brexpiprazole tablets if a clinically significant decline in WBC occurs in absence of other causative factors. (5.8)
- Orthostatic Hypotension and Syncope: Monitor heart rate and blood pressure and warn patients with known cardiovascular or cerebrovascular disease, and risk of dehydration or syncope. (5.9)
- Seizures: Use cautiously in patients with a history of seizures or with conditions that lower the seizure threshold. (5.11)

6 ADVERSE REACTIONS

Most common adverse reactions in adults were (6.1):

- MDD: Weight increased and akathisia (greater than or equal to 5% and at least twice the rate for placebo)
- Schizophrenia: Weight increased (greater than or equal to 4% and at least twice the rate for placebo)

To report SUSPECTED ADVERSE REACTIONS, contact Ajanta Pharma USA Inc. at 1-855-664-7744 or FDA at 1-800-FDA-1088 or www.fda.gov/medwatch.

7 DRUG INTERACTIONS

Factors | Dosage Adjustments for brexpiprazole tablets (2.5)
Strong CYP2D6* or CYP3A4 inhibitors | Administer half of usual dose.
Strong/moderate CYP2D6 with Strong/moderate CYP3A4 inhibitors | Administer a quarter of usual dose.
Known CYP2D6 poor metabolizers taking strong/moderate CYP3A4 inhibitors | Administer a quarter of usual dose.
Strong CYP3A4 inducers | Double the usual dose and further adjust based on clinical response.
*Brexpiprazole tablets may be administered without dosage adjustment in patients with MDD when administered with strong CYP2D6 inhibitors (e.g., paroxetine, fluoxetine).

8 USE IN SPECIFIC POPULATIONS

Pregnancy: May cause extrapyramidal and/or withdrawal symptoms in neonates with third trimester exposure (8.1)

Pediatric use information is approved for Otsuka Pharmaceutical Company, Ltd.’s Rexulti® (brexpiprazole) tablets. However, due to Otsuka Pharmaceutical Company, Ltd.’s marketing exclusivity rights, this drug product is not labeled with that information.

FULL PRESCRIBING INFORMATION

WARNING: INCREASED MORTALITY IN ELDERLY PATIENTS WITH DEMENTIA-RELATED PSYCHOSIS and SUICIDAL THOUGHTS AND BEHAVIORS

Increased Mortality in Elderly Patients with Dementia-Related Psychosis
Elderly patients with dementia-related psychosis treated with antipsychotic drugs are at an increased risk of death. Brexpiprazole tablets are not approved for the treatment of patients with dementia-related psychosis [see Warnings and Precautions (5.1)].

Suicidal Thoughts and Behaviors
Antidepressants increased the risk of suicidal thoughts and behaviors in patients aged 24 years and younger in short-term studies. Monitor closely for clinical worsening and for emergence of suicidal thoughts and behaviors. The safety and effectiveness of brexpiprazole tablets have not been established in pediatric patients with MDD [see Warnings and Precautions (5.2), Use in Specific Populations (8.4)].

1 INDICATIONS AND USAGE

Brexpiprazole tablets are indicated for:

- Adjunctive treatment of major depressive disorder (MDD) in adults.
- Treatment of schizophrenia in adults.

2 DOSAGE AND ADMINISTRATION

2.1 Adjunctive Treatment of Major Depressive Disorder (Adults)

The recommended starting dosage for brexpiprazole tablets as adjunctive treatment of MDD in adults is 0.5 mg or 1 mg once daily, taken orally with or without food [see Clinical Pharmacology (12.3)].

Titrate to 1 mg once daily, then up to the target dosage of 2 mg once daily. Dosage increases should occur at weekly intervals based on the patient’s clinical response and tolerability. The maximum recommended daily dosage is 3 mg. Periodically reassess to determine the continued need and appropriate dosage for treatment.

2.2 Treatment of Schizophrenia (Adults)

Adults

The recommended starting dosage for brexpiprazole tablets for the treatment of schizophrenia in adults is 1 mg once daily on Days 1 to 4, taken orally with or without food [see Clinical Pharmacology (12.3)]. Titrate to 2 mg once daily on Day 5 through Day 7, then to 4 mg on Day 8 based on the patient’s clinical response and tolerability. The recommended target brexpiprazole tablets dosage is 2 mg to 4 mg once daily. The maximum recommended daily dosage is 4 mg.

Pediatric use information is approved for Otsuka Pharmaceutical Company, Ltd.’s Rexulti® (brexpiprazole) tablets. However, due to Otsuka Pharmaceutical Company, LTD.’s marketing exclusivity rights, this drug product is not labeled with that information.

2.3 Dosage Adjustments for Hepatic Impairment

For patients with moderate to severe hepatic impairment (Child-Pugh score greater than or equal to 7), the maximum recommended dosage is 2 mg once daily for patients with MDD, and 3 mg once daily for patients with schizophrenia [see Use in Specific Populations (8.7), Clinical Pharmacology (12.3)].

2.4 Dosage Adjustments for Renal Impairment

For patients with moderate, severe, or end-stage renal impairment (creatinine clearance CrCl less than 60 mL/minute), the maximum recommended dosage is 2 mg once daily for patients with MDD and 3 mg once daily for patients with schizophrenia [see Use in Specific Populations (8.8), Clinical Pharmacology (12.3)].

2.5 Dosage Modifications for CYP2D6 Poor Metabolizers and for Concomitant Use with CYP Inhibitors or Inducers

Dosage adjustments are recommended in patients who are known cytochrome P450 (CYP) 2D6 poor metabolizers and in patients taking concomitant CYP3A4 inhibitors or CYP2D6 inhibitors or strong CYP3A4 inducers (see Table 1). If the coadministered drug is discontinued, adjust the brexpiprazole tablets dosage to its original level. If the coadministered CYP3A4 inducer is discontinued, reduce the brexpiprazole tablets dosage to the original level over 1 to 2 weeks [see Drug Interactions (7.1),Clinical Pharmacology (12.3)].

Table 1: Dosage Adjustments of Brexpiprazole Tablets for CYP2D6 Poor Metabolizers and for Concomitant Use with CYP3A4 and CYP2D6 Inhibitors and/or CYP3A4 Inducers
Factors | Adjusted Brexpiprazole Tablets Dosage
CYP2D6 Poor Metabolizers
CYP2D6 poor metabolizers | Administer half of the usual dose.
Known CYP2D6 poor metabolizers taking strong/moderate CYP3A4 inhibitors | Administer a quarter of the usual dose.
Patients Taking CYP2D6 Inhibitors and/or CYP3A4 Inhibitors
Strong CYP2D6 inhibitors* | Administer half of the usual dose.
Strong CYP3A4 inhibitors | Administer half of the usual dose.
Strong/moderate CYP2D6 inhibitors with strong/moderate CYP3A4 inhibitors | Administer a quarter of the usual dose.
Patients Taking CYP3A4 Inducers
Strong CYP3A4 inducers | Double usual dose over 1 to 2 weeks.
*In the clinical trials examining the adjunctive use of brexpiprazole tablets in the treatment of MDD, dosage was not adjusted for strong CYP2D6 inhibitors (e.g., paroxetine, fluoxetine). Thus, CYP considerations are already factored into general dosing recommendations, and brexpiprazole tablets may be administered without dosage adjustment in patients with MDD.

3 DOSAGE FORMS AND STRENGTHS

Brexpiprazole tablets are available in 6 strengths:

- 0.25 mg tablets are brown colored, round, biconvex, film-coated tablet, debossed with “BX” on one side and “6” on other side.
- 0.5 mg tablets are orange colored, round, biconvex, film-coated tablet, debossed with “BX” on one side and “5” on other side.
- 1 mg tablets are yellow colored, round, biconvex, film-coated tablet, debossed with “BX” on one side and “1” on other side.
- 2 mg tablets are light green to green colored, round, biconvex, film-coated tablet, debossed with “BX” on one side and “2” on other side.
- 3 mg tablets are pink colored, round, biconvex, film-coated tablet, debossed with “BX” on one side and “3” on other side.
- 4 mg tablets are white to off-white colored, round, biconvex, film-coated tablet, debossed with “BX” on one side and “4” on other side.

4 CONTRAINDICATIONS

Brexpiprazole tablets are contraindicated in patients with a known hypersensitivity to brexpiprazole or any of its components. Reactions have included rash, facial swelling, urticaria, and anaphylaxis.

5 WARNINGS AND PRECAUTIONS

5.1 Increased Mortality in Elderly Patients with Dementia-Related Psychosis

Elderly patients with dementia-related psychosis treated with antipsychotic drugs are at an increased risk of death. Analyses of 17 placebo-controlled trials (modal duration of 10 weeks), largely in patients taking atypical antipsychotic drugs, revealed a risk of death in drug-treated patients of between 1.6 to 1.7 times the risk of death in placebo-treated patients. Over the course of a typical 10-week controlled trial, the rate of death in drug-treated patients was about 4.5%, compared to a rate of about 2.6% in the placebo group.

Although the causes of death were varied, most of the deaths appeared to be either cardiovascular (e.g., heart failure, sudden death) or infectious (e.g., pneumonia) in nature. Brexpiprazole tablets are not approved for the treatment of patients with dementia-related psychosis [see Boxed Warning, Warnings and Precautions (5.3)].

5.2 Suicidal Thoughts and Behaviors in Children, Adolescents and Young Adults

In pooled analyses of placebo-controlled trials of antidepressant drugs (SSRIs and other antidepressant classes) that included approximately 77,000 adult patients and over 4400 pediatric patients, the incidence of suicidal thoughts and behaviors in patients age 24 years and younger was greater in antidepressant-treated patients than in placebo-treated patients. The drug-placebo differences in the number of cases of suicidal thoughts and behaviors per 1000 patients treated are provided in Table 2.

No suicides occurred in any of the pediatric studies. There were suicides in the adult studies, but the number was not sufficient to reach any conclusion about antidepressant drug effect on suicide.

Table 2: Risk Differences of the Number of Patients with Suicidal Thoughts or Behaviors in the Pooled Placebo-Controlled Trials of Antidepressants in Pediatric* and Adult Patients
Age Range (years) | Drug-Placebo Difference in Number of Patients with Suicidal Thoughts or Behaviors per 1000 Patients Treated
 | Increases Compared to Placebo
<18 | 14 additional patients
18 to 24 | 5 additional patients
 | Decreases Compared to Placebo
25 to 64 | 1 fewer patient
≥65 | 6 fewer patients
*Brexpiprazole tablets are not approved in pediatric patients with MDD.

It is unknown whether the risk of suicidal thoughts and behaviors in children, adolescents, and young adults extends to longer-term use, i.e., beyond four months. However, there is substantial evidence from placebo-controlled maintenance studies in adults with MDD that antidepressants delay the recurrence of depression.

Monitor all antidepressant-treated patients for clinical worsening and emergence of suicidal thoughts and behaviors, especially during the initial few months of drug therapy and at times of dosage changes. Counsel family members or caregivers of patients to monitor for changes in behavior and to alert the healthcare provider. Consider changing the therapeutic regimen, including possibly discontinuing brexpiprazole tablets, in patients whose depression is persistently worse or who are experiencing emergent suicidal thoughts or behaviors.

5.3 Cerebrovascular Adverse Reactions Including Stroke in Elderly Patients with Dementia-Related Psychosis

In placebo-controlled trials in elderly patients with dementia, patients randomized to risperidone, aripiprazole, and olanzapine had a higher incidence of stroke and transient ischemic attack, including fatal stroke. Brexpiprazole tablets are not approved for the treatment of patients with dementia-related psychosis [see Boxed Warning, Warnings and Precautions (5.1)].

5.4 Neuroleptic Malignant Syndrome (NMS)

A potentially fatal symptom complex, sometimes referred to as neuroleptic malignant syndrome (NMS), has been reported in association with administration of antipsychotic drugs, including brexpiprazole tablets. Clinical manifestations of NMS are hyperpyrexia, muscle rigidity, altered mental status, and evidence of autonomic instability. Additional signs may include elevated creatinine phosphokinase, myoglobinuria (rhabdomyolysis), and acute renal failure.

If NMS is suspected, immediately discontinue brexpiprazole tablets and provide intensive symptomatic treatment and monitoring.

5.5 Tardive Dyskinesia

Tardive dyskinesia, a syndrome consisting of potentially irreversible, involuntary, dyskinetic movements, may develop in patients treated with antipsychotic drugs. The risk appears to be highest among the elderly, especially elderly women, but it is not possible to predict which patients are likely to develop the syndrome. Whether antipsychotic drugs differ in their potential to cause tardive dyskinesia is unknown.

The risk of tardive dyskinesia and the likelihood that it will become irreversible increase with the duration of treatment and the cumulative dose. The syndrome can develop after a relatively brief treatment period, even at low doses. It may also occur after discontinuation of treatment.

Tardive dyskinesia may remit, partially or completely, if antipsychotic treatment is discontinued. Antipsychotic treatment itself, however, may suppress (or partially suppress) the signs and symptoms of the syndrome, possibly masking the underlying process. The effect that symptomatic suppression has upon the long-term course of tardive dyskinesia is unknown.

Given these considerations, brexpiprazole tablets should be prescribed in a manner most likely to reduce the risk of tardive dyskinesia. Chronic antipsychotic treatment should generally be reserved for patients: (1) who suffer from a chronic illness that is known to respond to antipsychotic drugs; and (2) for whom alternative, effective, but potentially less harmful treatments are not available or appropriate. In patients who do require chronic treatment, use the lowest dose and the shortest duration of treatment needed to produce a satisfactory clinical response. Periodically reassess the need for continued treatment.

If signs and symptoms of tardive dyskinesia appear in a patient on brexpiprazole tablets, drug discontinuation should be considered. However, some patients may require treatment with brexpiprazole tablets despite the presence of the syndrome.

5.6 Metabolic Changes

Atypical antipsychotic drugs, including brexpiprazole tablets, have caused metabolic changes, including hyperglycemia, diabetes mellitus, dyslipidemia, and body weight gain. Although all of the drugs in the class to date have been shown to produce some metabolic changes, each drug has its own specific risk profile.

Hyperglycemia and Diabetes Mellitus

Hyperglycemia, in some cases extreme and associated with ketoacidosis or hyperosmolar coma or death, has been reported in patients treated with atypical antipsychotics. There have been reports of hyperglycemia in patients treated with brexpiprazole tablets. Assess fasting plasma glucose before or soon after initiation of antipsychotic medication and monitor periodically during long-term treatment.

Major Depressive Disorder

In the 6-week placebo-controlled, fixed-dose clinical trials in adult patients with MDD, the proportions of patients with shifts in fasting glucose from normal (less than 100 mg/dL) to high (greater than or equal to 126 mg/dL) and borderline (greater than or equal to 100 and less than 126 mg/dL) to high were similar in patients treated with brexpiprazole tablets and placebo.

In the long-term, open-label depression studies, 5% of adult patients with normal baseline fasting glucose experienced a shift to high while taking brexpiprazole tablets plus an antidepressant (ADT); 25% of patients with borderline fasting glucose experienced shifts to high. Combined, 9% of patients with normal or borderline fasting glucose experienced shifts to high fasting glucose during the long-term depression studies.

Schizophrenia

Adults

In the 6-week placebo-controlled, fixed-dose clinical trials in adult patients with schizophrenia, the proportions of patients with shifts in fasting glucose from normal (less than 100 mg/dL) to high (greater than or equal to 126 mg/dL) or borderline (greater than or equal to 100 and less than 126 mg/dL) to high were similar in patients treated with brexpiprazole tablets and placebo.

In the long-term, open-label schizophrenia studies, 8% of adult patients with normal baseline fasting glucose experienced a shift from normal to high while taking brexpiprazole tablets; 17% of patients with borderline fasting glucose experienced shifts from borderline to high. Combined, 10% of patients with normal or borderline fasting glucose experienced shifts to high fasting glucose during the long-term schizophrenia studies.

Dyslipidemia

Atypical antipsychotics cause adverse alterations in lipids. Before or soon after initiation of antipsychotic medication, obtain a fasting lipid profile at baseline and monitor periodically during treatment.

Major Depressive Disorder

In the 6-week placebo-controlled, fixed-dose clinical trials in adult patients with MDD, changes in fasting total cholesterol, LDL cholesterol, and HDL cholesterol were similar in brexpiprazole tablets- and placebo-treated patients. Table 3 shows the proportions of patients with changes in fasting triglycerides.

Table 3: Change in Fasting Triglycerides in the 6-Week Placebo-Controlled, Fixed-Dose MDD Trials
Proportion of Patients with Shifts Baseline to Post-Baseline
Triglycerides | Placebo | 1 mg/day | 2 mg/day | 3 mg/day
Normal to High (˂150 mg/dL to ≥ 200 and ˂ 500 mg /dL) | 6% (15/257)* | 5% (7/145)* | 13% (15/115)* | 9% (13/150)*
Normal/Borderline to Very High (˂200 mg/dL to ≥ 500 mg/dL) | 0% (0/309)* | 0% (0/177)* | 0.7% (1/143)* | 0% (0/179)*
* denotes n/N where N=the total number of patients who had a measurement at baseline and at least one post-baseline result
n=the number of patients with shift

In the long-term, open-label depression studies, shifts in baseline fasting cholesterol from normal to high were reported in 9% (total cholesterol), 3% (LDL cholesterol), and shifts in baseline from normal to low were reported in 14% (HDL cholesterol) of patients taking brexpiprazole tablets. Of patients with normal baseline triglycerides, 17% experienced shifts to high, and 0.2% experienced shifts to very high. Combined, 0.6% of patients with normal or borderline fasting triglycerides experienced shifts to very high fasting triglycerides during the long-term depression studies.

Schizophrenia

Adults

In the 6-week placebo-controlled, fixed-dose clinical trials in adult patients with schizophrenia, changes in fasting total cholesterol, LDL cholesterol, and HDL cholesterol were similar in brexpiprazole tablets- and placebo-treated patients. Table 4 shows the proportions of patients with changes in fasting triglycerides.

Table 4: Change in Fasting Triglycerides in the 6-Week Placebo-Controlled, Fixed-Dose Schizophrenia Trials in Adult Patients
Proportion of Patients with Shifts Baseline to Post-Baseline
Triglycerides | Placebo | 1 mg/day | 2 mg/day | 4 mg/day
Normal to High (˂150 mg/dL to ≥ 200 and ˂ 500 mg /dL) | 6% (15/253)* | 10% (7/72)* | 8% (19/232)* | 10% (22/226)*
Normal/Borderline to Very High (˂200 mg/dL to ≥ 500 mg/dL) | 0% (0/303)* | 0% (0/94)* | 0% (0/283)* | 0.4% (1/283)*
* denotes n/N where N=the total number of patients who had a measurement at baseline and at least one post-baseline result
n=the number of patients with shift

In the long-term, open-label schizophrenia studies in adult patients, shifts in baseline fasting cholesterol from normal to high were reported in 6% (total cholesterol), 2% (LDL cholesterol), and shifts in baseline from normal to low were reported in 17% (HDL cholesterol) of patients taking brexpiprazole tablets. Of patients with normal baseline triglycerides, 13% experienced shifts to high, and 0.4% experienced shifts to very high triglycerides. Combined, 0.6% of patients with normal or borderline fasting triglycerides experienced shifts to very high fasting triglycerides during the long-term schizophrenia studies.

Weight Gain

Weight gain has been observed in patients treated with atypical antipsychotics, including brexpiprazole tablets. Monitor weight at baseline and frequently thereafter.

Major Depressive Disorder

Table 5 shows weight gain data at last visit and percentage of adult patients with greater than or equal to 7% increase in body weight at endpoint from the 6-week placebo-controlled, fixed-dose clinical studies in patients with MDD.

Table 5: Increases in Body Weight in the 6-Week Placebo-Controlled, Fixed-Dose MDD Trials
 | Placebo n=407 | 1 mg/day n=225 | 2mg/day n=187 | 3mg/day n=228
Mean Change from Baseline (kg) at Last Visit
All Patients | +0.3 | +1.3 | +1.6 | +1.6
Proportion of Patients with a ≥7% Increase in Body Weight (kg) at Any Visit (*n/N)
 | 2% | 5% | 5% | 2%
 | (8/407)* | (11/225)* | (9/187)* | (5/228)*
* N=the total number of patients who had a measurement at baseline and at least one post-baseline result
n=the number of patients with a shift greater than or equal to 7%

In the long-term, open-label depression studies, 4% of patients discontinued due to weight increase. Brexpiprazole tablets was associated with mean change from baseline in weight of 2.9 kg at Week 26 and 3.1 kg at Week 52. In the long-term, open-label depression studies, 30% of patients demonstrated a greater than or equal to 7% increase in body weight, and 4% demonstrated a greater than or equal to 7% decrease in body weight.

Schizophrenia

Adults

Table 6 shows weight gain data at last visit and percentage of adult patients with greater than or equal to 7% increase in body weight at endpoint from the 6-week placebo-controlled, fixed-dose clinical studies in adult patients with schizophrenia.

Table 6: Increases in Body Weight in the 6-Week Placebo-Controlled, Fixed-Dose Schizophrenia Trials in Adult Patients
 | Placebo n=362 | 1 mg/day n=120 | 2mg/day n=362 | 4mg/day n=362
Mean Change from Baseline (kg) at Last Visit
All Patients | +0.2 | +1.0 | +1.2 | +1.2
Proportion of Patients with a ≥7% Increase in Body Weight (kg) at Any Visit (*n/N)
 | 4% | 10% | 11% | 10%
 | (15/362)* | (12/120)* | (38/362)* | (37/362)*
* denotes n/N where N=the total number of patients who had a measurement at baseline and at least one post-baseline result
n=the number of patients with a shift greater than or equal to 7%

In the long-term, open-label schizophrenia studies in adult patients, 0.6% of patients discontinued due to weight increase. Brexpiprazole tablets was associated with mean change from baseline in weight of 1.3 kg at Week 26 and 2.0 kg at Week 52. In the long-term, open label schizophrenia studies, 20% of patients demonstrated a greater than or equal to 7% increase in body weight, and 10% demonstrated a greater than or equal to 7% decrease in body weight.

Pediatric use information is approved for Otsuka Pharmaceutical Company, Ltd.’s Rexulti® (brexpiprazole) tablets. However, due to Otsuka Pharmaceutical Company, LTD.’s marketing exclusivity rights, this drug product is not labeled with that information.

5.7 Pathological Gambling and Other Compulsive Behaviors

Post-marketing case reports suggest that patients can experience intense urges, particularly for gambling, and the inability to control these urges while taking brexpiprazole tablets. Other compulsive urges, reported less frequently, include sexual urges, shopping, eating, or binge eating, and other impulsive or compulsive behaviors. Because patients may not recognize these behaviors as abnormal, it is important for prescribers to ask patients or their caregivers specifically about the development of new or intense gambling urges, compulsive sexual urges, compulsive shopping, binge or compulsive eating, or other urges while being treated with brexpiprazole tablets. In some cases, although not all, urges were reported to have stopped when the dose was reduced, or the medication was discontinued. Compulsive behaviors may result in harm to the patient and others if not recognized. Consider dose reduction or stopping the medication if a patient develops such urges.

5.8 Leukopenia, Neutropenia, and Agranulocytosis

Leukopenia and neutropenia have been reported during treatment with antipsychotic agents. Agranulocytosis (including fatal cases) has been reported with other agents in this class.

Possible risk factors for leukopenia and neutropenia include pre-existing low white blood cell count (WBC) or absolute neutrophil count (ANC) and history of drug-induced leukopenia or neutropenia. In patients with a pre-existing low WBC or ANC or a history of drug-induced leukopenia or neutropenia, perform a complete blood count (CBC) frequently during the first few months of therapy. In such patients, consider discontinuation of brexpiprazole tablets at the first sign of a clinically significant decline in WBC in the absence of other causative factors.

Monitor patients with clinically significant neutropenia for fever or other symptoms or signs of infection and treat promptly if such symptoms or signs occur. Discontinue brexpiprazole tablets in patients with absolute neutrophil count less than 1000/mm^3 and follow their WBC until recovery.

5.9 Orthostatic Hypotension and Syncope

Atypical antipsychotics cause orthostatic hypotension and syncope. Generally, the risk is greatest during initial dose titration and when increasing the dose. In the short-term, placebo-controlled clinical studies of brexpiprazole tablets plus ADT in adult patients with MDD, the incidence of orthostatic hypotension-related adverse reactions in brexpiprazole tablets plus ADT-treated patients compared to placebo plus ADT-treated patients included: dizziness (2% versus 2%) and orthostatic hypotension (0.1% versus 0%). In the short-term, placebo-controlled clinical studies of brexpiprazole tablets in adult patients with schizophrenia, the incidence of orthostatic hypotension-related adverse reactions in brexpiprazole tablets-treated patients compared to placebo patients included: dizziness (2% versus 2%), orthostatic hypotension (0.4% versus 0.2%), and syncope (0.1% versus 0%).

Orthostatic vital signs should be monitored in patients who are vulnerable to hypotension (e.g., elderly patients, patients with dehydration, hypovolemia, concomitant treatment with antihypertensive medication), patients with known cardiovascular disease (history of myocardial infarction, ischemic heart disease, heart failure, or conduction abnormalities), and patients with cerebrovascular disease. Brexpiprazole tablets has not been evaluated in patients with a recent history of myocardial infarction or unstable cardiovascular disease. Such patients were excluded from the premarketing clinical trials.

5.10 Falls

Antipsychotics, including brexpiprazole tablets, may cause somnolence, postural hypotension, motor, and sensory instability, which may lead to falls and, consequently, fractures or other injuries. For patients with diseases, conditions, or medications that could exacerbate these effects, complete fall risk assessments when initiating antipsychotic treatment and recurrently for patients on long-term antipsychotic therapy.

5.11 Seizures

Like other antipsychotic drugs, brexpiprazole tablets may cause seizures. This risk is greatest in patients with a history of seizures or with conditions that lower the seizure threshold. Conditions that lower the seizure threshold may be more prevalent in older patients.

5.12 Body Temperature Dysregulation

Atypical antipsychotics may disrupt the body’s ability to reduce core body temperature. Strenuous exercise, exposure to extreme heat, dehydration, and anticholinergic medications may contribute to an elevation in core body temperature; use brexpiprazole tablets with caution in patients who may experience these conditions.

5.13 Dysphagia

Esophageal dysmotility and aspiration have been associated with antipsychotic drug use. Antipsychotic drugs, including brexpiprazole tablets, should be used cautiously in patients at risk for aspiration.

5.14 Potential for Cognitive and Motor Impairment

Brexpiprazole tablets, like other antipsychotics, has the potential to impair judgment, thinking, or motor skills. In the 6-week placebo-controlled clinical trials in patients with MDD, somnolence (including sedation and hypersomnia) was reported in 4% of brexpiprazole tablets plus ADT-treated patients compared to 1% of placebo plus ADT-treated patients.

In the 6-week placebo-controlled clinical trials in adult patients with schizophrenia, somnolence (including sedation and hypersomnia) was reported in 5% of brexpiprazole tablets-treated patients compared to 3% of placebo-treated patients.

Patients should be cautioned about operating hazardous machinery, including motor vehicles, until they are reasonably certain that brexpiprazole tablets therapy does not affect them adversely.

6 ADVERSE REACTIONS

The following adverse reactions are discussed in more detail in other sections of the labeling:

- Increased Mortality in Elderly Patients with Dementia-Related Psychosis [see Boxed Warning, Warnings and Precautions (5.1)]
- Suicidal Thoughts and Behaviors in Adolescents and Young Adults [see Boxed Warning, Warnings and Precautions (5.2)]
- Cerebrovascular Adverse Reactions Including Stroke in Elderly Patients with Dementia-Related Psychosis [see Warnings and Precautions (5.3)]
- Neuroleptic Malignant Syndrome (NMS) [see Warnings and Precautions (5.4)]
- Tardive Dyskinesia [see Warnings and Precautions (5.5)]
- Metabolic Changes [see Warnings and Precautions (5.6)]
- Pathological Gambling and Other Compulsive Behaviors [see Warnings and Precautions (5.7)]
- Leukopenia, Neutropenia, and Agranulocytosis [see Warnings and Precautions (5.8)]
- Orthostatic Hypotension and Syncope [see Warnings and Precautions (5.9)]
- Falls [see Warnings and Precautions (5.10)]
- Seizures [see Warnings and Precautions (5.11)]
- Body Temperature Dysregulation [see Warnings and Precautions (5.12)]
- Dysphagia [see Warnings and Precautions (5.13)]
- Potential for Cognitive and Motor Impairment [see Warnings and Precautions (5.14)]

6.1 Clinical Trial Experience

Because clinical trials are conducted under widely varying conditions, adverse reaction rates observed in the clinical trials of a drug cannot be directly compared to rates in the clinical trials of another drug and may not reflect the rates observed in clinical practice.

Major Depressive Disorder

The safety of brexpiprazole tablets was evaluated in 1054 adult patients (18 to 65 years of age) diagnosed with MDD who participated in two 6-week placebo-controlled, fixed-dose clinical trials in patients with major depressive disorder in which brexpiprazole tablets was administered at doses of 1 mg to 3 mg daily as adjunctive treatment to continued antidepressant therapy; patients in the placebo group continued to receive antidepressant therapy [see Clinical Studies (14.1)].

Adverse Reactions Reported as Reasons for Discontinuation of Treatment

A total of 3% (17/643) of brexpiprazole tablets-treated patients and 1% (3/411) of placebo-treated patients discontinued due to adverse reactions.

Common Adverse Reactions

Adverse reactions associated with the adjunctive use of brexpiprazole tablets (incidence of 2% or greater and adjunctive brexpiprazole tablets incidence greater than adjunctive placebo) that occurred during acute therapy (up to 6-weeks in patients with MDD) are shown in Table 7.

Table 7: Adverse Reactions in Pooled 6-Week Placebo-Controlled, Fixed-Dose MDD Trials in Adults (Studies 1 and 2)*
 | Placebo (N=411) | Brexpiprazole Tablets
 | Placebo (N=411) | 1 mg/day (N=226) | 2 mg/day (N=188) | 3 mg/day (N=229) | All Brexpiprazole Tablets (N=643)
Gastrointestinal Disorders
Constipation | 1% | 3% | 2% | 1% | 2%
General Disorders and Administration Site Conditions
Fatigue | 2% | 3% | 2% | 5% | 3%
Infections and Infestations
Nasopharyngitis | 2% | 7% | 1% | 3% | 4%
Investigations
Weight Increased | 2% | 7% | 8% | 6% | 7%
Blood Cortisol Decreased | 1% | 4% | 0% | 3% | 2%
Metabolism and Nutrition
Increased Appetite | 2% | 3% | 3% | 2% | 3%
Nervous System Disorders
Akathisia | 2% | 4% | 7% | 14% | 9%
Headache | 6% | 9% | 4% | 6% | 7%
Somnolence | 0.5% | 4% | 4% | 6% | 5%
Tremor | 2% | 4% | 2% | 5% | 4%
Dizziness | 1% | 1% | 5% | 2% | 3%
Psychiatric Disorders
Anxiety | 1% | 2% | 4% | 4% | 3%
Restlessness | 0% | 2% | 3% | 4% | 3%

* Adverse reactions that occurred in greater than or equal to 2% of brexpiprazole tablets-treated patients and greater incidence than in placebo-treated patients

Dose-Related Adverse Reactions in the MDD Trials

In Studies 1 and 2, among the adverse reactions that occurred at greater than or equal to 2% incidence in the patients treated with brexpiprazole tablets plus ADT, the incidences of akathisia and restlessness increased with increases in dose.

Schizophrenia

Adults

The safety of brexpiprazole tablets was evaluated in 852 adult patients (18 to 65 years of age) diagnosed with schizophrenia who participated in two 6-week placebo-controlled, fixed-dose clinical trials in which brexpiprazole tablets was administered at daily doses of 1 mg, 2 mg and 4 mg [see Clinical Studies (14.2)].

Common Adverse Reactions

Adverse reactions associated with brexpiprazole tablets (incidence of 2% or greater and brexpiprazole tablets incidence greater than placebo) during short-term (up to 6 weeks) trials in adult patients with schizophrenia are shown in Table 8.

Table 8: Adverse Reactions in Pooled 6-Week Placebo-Controlled, Fixed-Dose Schizophrenia Trials in Adult Patients (Studies 3 and 4)*
 | Placebo (N=368) | Brexpiprazole Tablets
 | Placebo (N=368) | 1 mg/day (N=120) | 2 mg/day (N=368) | 4 mg/day (N=364) | ALL Brexpiprazole Tablets (N=852)
Gastrointestinal Disorders
Dyspepsia | 2% | 6% | 2% | 3% | 3%
Diarrhea | 2% | 1% | 3% | 3% | 3%
Investigations
Weight Increased | 2% | 3% | 4% | 4% | 4%
Blood Creatinine Phosphokinase Increased | 1% | 4% | 2% | 2% | 2%
Nervous System Disorders
Akathisia | 5% | 4% | 5% | 7% | 6%
Tremor | 1% | 2% | 2% | 3% | 3%
Sedation | 1% | 2% | 2% | 3% | 2%

* Adverse reactions that occurred in greater than or equal to 2% of brexpiprazole tablets-treated patients and greater incidence than in placebo-treated patients

Extrapyramidal Symptoms

Major Depressive Disorder

The incidence of reported extrapyramidal symptoms (EPS)-related adverse reactions, excluding akathisia, was 6% for brexpiprazole tablets plus ADT-treated patients versus 3% for placebo plus ADT-treated patients. The incidence of akathisia events for brexpiprazole tablets plus ADT-treated patients was 9% versus 2% for placebo plus ADT-treated patients.

In the 6-week placebo-controlled MDD studies, data was objectively collected on the Simpson-Angus Rating Scale (SAS) for EPS, the Barnes Akathisia Rating Scale (BARS) for akathisia and the Abnormal Involuntary Movement Score (AIMS) for dyskinesia. The mean change from baseline at last visit for brexpiprazole tablets plus ADT-treated patients for the SAS, BARS and AIMS was comparable to placebo-treated patients. The percentage of patients who shifted from normal to abnormal was greater in brexpiprazole tablets plus ADT-treated patients versus placebo plus ADT-treated patients for the BARS (4% versus 0.6%) and the SAS (4% versus 3%).

Schizophrenia

The incidence of reported EPS-related adverse reactions, excluding akathisia, was 5% for brexpiprazole tablets-treated patients versus 4% for placebo-treated patients. The incidence of akathisia events for brexpiprazole tablets-treated patients was 6% versus 5% for placebo-treated patients.

In the 6-week placebo-controlled, fixed-dose schizophrenia studies in adults, data was objectively collected on the Simpson-Angus Rating Scale (SAS) for EPS, the Barnes Akathisia Rating Scale (BARS) for akathisia and the Abnormal Involuntary Movement Scale (AIMS) for dyskinesia. The mean change from baseline at last visit for brexpiprazole tablets-treated patients for the SAS, BARS and AIMS was comparable to placebo-treated patients. The percentage of patients who shifted from normal to abnormal was greater in brexpiprazole tablets-treated patients versus placebo for the BARS (2% versus 1%) and the SAS (7% versus 5%).

Dystonia

Symptoms of dystonia may occur in susceptible individuals during the first few days of treatment. Dystonic symptoms include spasm of the neck muscles, sometimes progressing to tightness of the throat, swallowing difficulty, difficulty breathing, and/or protrusion of the tongue. While these symptoms can occur at low doses, they occur more frequently and with greater severity with high potency and at higher doses of first-generation antipsychotic drugs. An elevated risk of acute dystonia is observed in males and younger age groups.

Other Adverse Reactions Observed during the Premarketing Evaluation of Brexpiprazole Tablets

Other adverse reactions (greater than or equal to 1% frequency and greater than placebo) within the short-term, placebo-controlled trials in adult patients with MDD and schizophrenia are shown below. The following listing does not include adverse reactions: 1) already listed in previous tables or elsewhere in the labeling, 2) for which a drug cause was remote, 3) which were so general as to be uninformative, 4) which were not considered to have clinically significant implications, or 5) which occurred at a rate equal to or less than placebo.

Eye Disorders: Vision Blurred

Gastrointestinal Disorders: Nausea, Dry Mouth, Salivary Hypersecretion, Abdominal Pain, Flatulence

Infections and Infestations: Urinary Tract Infection

Investigations: Blood Prolactin Increased

Musculoskeletal and Connective Tissue Disorders: Myalgia

Psychiatric Disorders: Abnormal Dreams, Insomnia

Skin and Subcutaneous Tissue Disorders: Hyperhidrosis

Pediatric use information is approved for Otsuka Pharmaceutical Company, Ltd.’s Rexulti® (brexpiprazole) tablets. However, due to Otsuka Pharmaceutical Company, LTD.’s marketing exclusivity rights, this drug product is not labeled with that information.

6.2 Postmarketing Experience

The following adverse reaction has been identified during post-approval use of brexpiprazole tablets. Because these reactions are reported voluntarily from a population of uncertain size, it is not always possible to reliably estimate their frequency or establish a causal relationship to drug exposure.

Nervous System disorders: Neuroleptic Malignant Syndrome

7 DRUG INTERACTIONS

7.1 Drugs Having Clinically Important Interactions with Brexpiprazole Tablets

Table 9: Clinically Important Drug Interactions with Brexpiprazole Tablets
Strong CYP3A4 Inhibitors
Clinical Impact: | Concomitant use of brexpiprazole tablets with strong CYP3A4 inhibitors increased the exposure of brexpiprazole compared to the use of brexpiprazole tablets alone [see Clinical Pharmacology (12.3)].
Intervention: | With concomitant use of brexpiprazole tablets with a strong CYP3A4 inhibitor, reduce the brexpiprazole tablets dosage [see Dosage and Administration (2.5)].
Strong CYP2D6 Inhibitors*
Clinical Impact: | Concomitant use of brexpiprazole tablets with strong CYP2D6 inhibitors increased the exposure of brexpiprazole compared to the use of brexpiprazole tablets alone [see Clinical Pharmacology (12.3)].
Intervention: | With concomitant use of brexpiprazole tablets with a strong CYP2D6 inhibitor, reduce the brexpiprazole tablets dosage [see Dosage and Administration (2.5)].
Both CYP3A4 Inhibitors and CYP2D6 Inhibitors
Clinical Impact: | Concomitant use of brexpiprazole tablets with 1) a strong CYP3A4 inhibitor and a strong CYP2D6 inhibitor; or 2) a moderate CYP3A4 inhibitor and a strong CYP2D6 inhibitor; or 3) a strong CYP3A4 inhibitor and a moderate CYP2D6 inhibitor; or 4) a moderate CYP3A4 inhibitor and a moderate CYP2D6 inhibitor, increased the exposure of brexpiprazole compared to the use of brexpiprazole tablets alone [see Clinical Pharmacology (12.3)] .
Intervention: | With concomitant use of brexpiprazole tablets with 1) a strong CYP3A4 inhibitor and a strong CYP2D6 inhibitor; or 2) a moderate CYP3A4 inhibitor and a strong CYP2D6 inhibitor; or 3) a strong CYP3A4 inhibitor and a moderate CYP2D6 inhibitor; or 4) a moderate CYP3A4 inhibitor and a moderate CYP2D6 inhibitor, decrease the brexpiprazole tablets dosage [see Dosage and Administration (2.5)] .
Strong CYP3A4 Inducers
Clinical Impact: | Concomitant use of brexpiprazole tablets and a strong CYP3A4 inducer decreased the exposure of brexpiprazole compared to the use of brexpiprazole tablets alone [see Clinical Pharmacology (12.3)].
Intervention: | With concomitant use of brexpiprazole tablets with a strong CYP3A4 inducer, increase the brexpiprazole tablets dosage [see Dosage and Administration (2.5)].
* In the clinical trials examining the adjunctive use of brexpiprazole tablets in the treatment of MDD, dosage was not adjusted for strong CYP2D6 inhibitors (e.g., paroxetine, fluoxetine). Thus, CYP considerations are already factored into general dosing recommendations, and brexpiprazole tablets may be administered without dosage adjustment in patients with MDD.

7.2 Drugs Having No Clinically Important Interactions with Brexpiprazole Tablets

Based on pharmacokinetic studies, no dosage adjustment of brexpiprazole tablets is required when administered concomitantly with CYP2B6 inhibitors (e.g., ticlopidine) or gastric pH modifiers (e.g., omeprazole). Additionally, no dosage adjustment for substrates of CYP2D6 (e.g., dextromethorphan), CYP3A4 (e.g., lovastatin), CYP2B6 (e.g., bupropion), BCRP (e.g., rosuvastatin), or P-gp (e.g., fexofenadine) is required when administered concomitantly with brexpiprazole tablets.

8 USE IN SPECIFIC POPULATIONS

8.1 Pregnancy

Pregnancy Exposure Registry

There is a pregnancy exposure registry that monitors pregnancy outcomes in women exposed to brexpiprazole tablets during pregnancy. For more information contact the National Pregnancy Registry for Atypical Antipsychotics at 1-866-961-2388 or visit http://womensmentalhealth.org/clinical-and-research-programs/pregnancyregistry/.

Risk Summary

Adequate and well-controlled studies have not been conducted with brexpiprazole tablets in pregnant women to inform drug-associated risks. However, neonates whose mothers are exposed to antipsychotic drugs, like brexpiprazole tablets, during the third trimester of pregnancy are at risk for extrapyramidal and/or withdrawal symptoms. In animal reproduction studies, no teratogenicity was observed with oral administration of brexpiprazole to pregnant rats and rabbits during organogenesis at doses up to 73 and 146 times, respectively, of maximum recommended human dose (MRHD) of 4 mg/day on a mg/m^2 basis. However, when pregnant rats were administered brexpiprazole during the period of organogenesis through lactation, the number of perinatal deaths of pups was increased at 73 times the MRHD [see Data]. The background risk of major birth defects and miscarriage for the indicated population(s) is unknown. In the U.S. general population, the estimated background risk of major birth defects and miscarriage in clinically recognized pregnancies is 2% to 4% and 15% to 20%, respectively.

Clinical Considerations

Fetal/Neonatal Adverse Reactions

Extrapyramidal and/or withdrawal symptoms, including agitation, hypertonia, hypotonia, tremor, somnolence, respiratory distress and feeding disorder, have been reported in neonates whose mothers were exposed to antipsychotic drugs during the third trimester of pregnancy. These symptoms have varied in severity. Some neonates recovered within hours or days without specific treatment; others required prolonged hospitalization. Monitor neonates for extrapyramidal and/or withdrawal symptoms and manage symptoms appropriately.

Data

Animal Data

Pregnant rats were treated with oral doses of 3 mg/kg/day, 10 mg/kg/day, and 30 mg/kg/day (7.3, 24, and 73 times the MRHD on a mg/m^2 basis) of brexpiprazole during the period of organogenesis. Brexpiprazole was not teratogenic and did not cause adverse developmental effects at doses up to 73 times the MRHD.

Pregnant rabbits were treated with oral doses of 10 mg/kg/day, 30 mg/kg/day, and 150 mg/kg/day (49, 146, and 730 times the MRHD) of brexpiprazole during the period of organogenesis. Brexpiprazole was not teratogenic and did not cause adverse developmental effects at doses up to 146 times the MRHD. Findings of decreased body weight, retarded ossification, and increased incidences of visceral and skeletal variations were observed in fetuses at 730 times the MRHD, a dose that induced maternal toxicity.

In a study in which pregnant rats were administered oral doses of 3 mg/kg/day, 10 mg/kg/day, and 30 mg/kg/day (7.3, 24, and 73 times the MRHD) during the period of organogenesis and through lactation, the number of live-born pups was decreased, and early postnatal deaths increased at a dose 73 times the MRHD. Impaired nursing by dams, and low birth weight and decreased body weight gain in pups were observed at 73 times, but not at 24 times, the MRHD.

8.2 Lactation

Risk Summary

Lactation studies have not been conducted to assess the presence of brexpiprazole in human milk, the effects of brexpiprazole on the breastfed infant, or the effects of brexpiprazole on milk production. Brexpiprazole is present in rat milk. The development and health benefits of breastfeeding should be considered along with the mother’s clinical need for brexpiprazole tablets and any potential adverse effects on the breastfed infant from brexpiprazole tablets or from the underlying maternal condition.

8.4 Pediatric Use

Major Depressive Disorder
Safety and effectiveness in pediatric patients with major depressive disorder have not been established. Antidepressants increased the risk of suicidal thoughts and behaviors in pediatric patients [see Boxed Warning, Warnings and Precautions (5.2)].

Pediatric use information is approved for Otsuka Pharmaceutical Company, Ltd.’s Rexulti® (brexpiprazole) tablets. However, due to Otsuka Pharmaceutical Company, LTD.’s marketing exclusivity rights, this drug product is not labeled with that information.

8.5 Geriatric Use

Clinical studies of the efficacy of brexpiprazole tablets did not include any patients aged 65 or older to determine whether they respond differently from younger patients. In general, dose selection for an elderly patient should be cautious, usually starting at the low end of the dosing range, reflecting the greater frequency of decreased hepatic, renal, and cardiac function, concomitant diseases, and other drug therapy.

Based on the results of a safety, tolerability, and pharmacokinetics trial, the pharmacokinetics of once daily oral administration of brexpiprazole (up to 3 mg/day for 14 days) as an adjunct therapy in the treatment of elderly patients (70 to 85 years old, N=11) with MDD were comparable to those observed in adult patients with MDD.

Antipsychotic drugs increase the risk of death in elderly patients with dementia-related psychosis. Brexpiprazole tablets are not approved for the treatment of patients with dementia-related psychosis [see Boxed Warning, Warnings and Precautions (5.1)].

8.6 CYP2D6 Poor Metabolizers

Dosage adjustment is recommended in known CYP2D6 poor metabolizers, because these patients have higher brexpiprazole concentrations than normal metabolizers of CYP2D6. Approximately 8% of Caucasians and 3% to 8% of Black/African Americans cannot metabolize CYP2D6 substrates and are classified as poor metabolizers [see Dosage and Administration (2.5), Clinical Pharmacology (12.3)].

8.7 Hepatic Impairment

Reduce the maximum recommended dosage in patients with moderate to severe hepatic impairment (Child-Pugh score greater than or equal to 7). Patients with moderate to severe hepatic impairment (Child-Pugh score greater than or equal to 7) generally had higher exposure to brexpiprazole than patients with normal hepatic function [see Clinical Pharmacology (12.3)]. Greater exposure may increase the risk of brexpiprazole tablets-associated adverse reactions [see Dosage and Administration (2.3)].

8.8 Renal Impairment

Reduce the maximum recommended dosage in patients with moderate, severe, or end-stage renal impairment (CrCl less than 60 mL/minute). Patients with impaired renal function (CrCl less than 60 mL/minute) had higher exposure to brexpiprazole than patients with normal renal function [see Clinical Pharmacology (12.3)]. Greater exposure may increase the risk of brexpiprazole tablets-associated adverse reactions [see Dosage and Administration (2.4)].

8.9 Other Specific Populations

No dosage adjustment for brexpiprazole tablets is required on the basis of a patient’s sex, race, or smoking status [see Clinical Pharmacology (12.3)].

9 DRUG ABUSE AND DEPENDENCE

9.1 Controlled Substance

Brexpiprazole is not a controlled substance.

9.2 Abuse

Animals given access to brexpiprazole tablets did not self-administer the drug, suggesting that brexpiprazole tablets does not have rewarding properties.

9.3 Dependence

Humans and animals that received chronic brexpiprazole tablets administration did not demonstrate any withdrawal signs upon drug discontinuation. This suggests that brexpiprazole tablets does not produce physical dependence.

10 OVERDOSAGE

There is limited clinical trial experience regarding human overdosage with brexpiprazole tablets.

Consult a Certified Poison Control Center (1-800-222-1222 or www.poison.org) for up-to-date guidance and advice regarding a brexpiprazole tablets overdosage. Management of overdose should concentrate on supportive therapy, maintaining an adequate airway, oxygenation and ventilation, and management of symptoms. Close medical supervision and monitoring should continue until the patient recovers.

Charcoal
Oral activated charcoal and sorbitol (50 g/240 mL), administered one hour after ingesting oral brexpiprazole, decreased brexpiprazole Cmax and area under the curve (AUC) by approximately 5% to 23% and 31% to 39% respectively; however, there is insufficient information available on the therapeutic potential of activated charcoal in treating an overdose with brexpiprazole tablets.

Hemodialysis
There is no information on the effect of hemodialysis in treating an overdose with brexpiprazole tablets; hemodialysis is unlikely to be useful because brexpiprazole is highly bound to plasma proteins.

11 DESCRIPTION

Brexpiprazole, an atypical antipsychotic, is available as brexpiprazole tablets. Brexpiprazole is 7-{4-[4-(1- Benzothiophen-4-yl)piperazin-1-yl]butoxy}quinolin-2(1H)-one. The molecular formula is C25H27N3O2S and its molecular weight is 433.57. The chemical structure is:

Brexpiprazole tablets are for oral administration and are available in 0.25 mg, 0.5 mg, 1 mg, 2 mg, 3 mg and 4 mg strengths. Inactive ingredients include microcrystalline cellulose, lactose monohydrate, low-substituted hydroxypropyl cellulose, hydroxypropyl cellulose, magnesium stearate, hypromellose, talc, propylene glycol, polyethylene glycol. Colorants includes titanium dioxide, iron oxide red (0.25 mg and 3 mg), FD&C Yellow #6 (0.5 mg), iron oxide yellow (1 mg, 2 mg and 3 mg), FD&C Blue #2 (2 mg).

12 CLINICAL PHARMACOLOGY

12.1 Mechanism of Action

The mechanism of action of brexpiprazole in the treatment of major depressive disorder or schizophrenia is unknown. However, the efficacy of brexpiprazole may be mediated through a combination of partial agonist activity at serotonin 5-HT1A and dopamine D2 receptors, and antagonist activity at serotonin 5-HT2A receptors.

12.2 Pharmacodynamics

Brexpiprazole has affinity (expressed as Ki) for multiple monoaminergic receptors including serotonin 5-HT1A (0.12 nM), 5-HT2A (0.47 nM), 5-HT2B (1.9 nM), 5-HT7 (3.7 nM), dopamine D2 (0.30 nM), D3 (1.1 nM), and noradrenergic α1A (3.8 nM), α1B (0.17 nM), α1D (2.6 nM), and α2C (0.59 nM) receptors. Brexpiprazole acts as a partial agonist at the 5-HT1A, D2, and D3 receptors and as an antagonist at 5-HT2A, 5-HT2B, 5-HT7, α1A, α1B, α1D, and α2C receptors. Brexpiprazole also exhibits affinity for histamine H1 receptor (19 nM) and for muscarinic M1 receptor (67% inhibition at 10 µM).

Cardiac Electrophysiology

At a dose 3 times the MRHD for the treatment of schizophrenia and 4 times the MRHD for adjunctive therapy to antidepressants for the treatment of MDD, brexpiprazole tablets does not prolong the QTc interval to any clinically relevant extent.

12.3 Pharmacokinetics

Absorption
After single-dose administration of brexpiprazole tablets, the peak plasma brexpiprazole concentrations occurred within 4 hours after administration, and the absolute oral bioavailability was 95%. Brexpiprazole steady-state concentrations were attained within 10 to 12 days of dosing.

Brexpiprazole tablets can be administered with or without food. Administration of a 4 mg brexpiprazole tablet with a standard high-fat meal did not significantly affect the Cmax or AUC of brexpiprazole. After single and multiple once daily dose administration, brexpiprazole exposure (Cmax and AUC) increased in proportion to the dose administered. In vitro studies of brexpiprazole did not indicate that brexpiprazole is a substrate of efflux transporters such as MDRI (P-gp) and BCRP.

Distribution
The volume of distribution of brexpiprazole following intravenous administration is high (1.56±0.42 L/kg), indicating extravascular distribution. Brexpiprazole is highly protein bound in plasma (greater than 99%) to serum albumin and α1-acid glycoprotein, and its protein binding is not affected by renal or hepatic impairment. Based on results of in vitro studies, brexpiprazole protein binding is not affected by warfarin, diazepam, or digitoxin.

Elimination
Metabolism
Based on in vitro metabolism studies of brexpiprazole using recombinant human cytochrome P450 (CYP1A1, 1A2, 2A6, 2B6, 2C8, 2C9, 2C19, 2D6, 2E1, and 3A4), the metabolism of brexpiprazole was shown to be mainly mediated by CYP3A4 and CYP2D6.

In vivo brexpiprazole is metabolized primarily by CYP3A4 and CYP2D6 enzymes. After single- and multiple-dose administrations, brexpiprazole and its major metabolite, DM-3411, were the predominant drug moieties in the systemic circulation. At steady-state, DM-3411 represented 23% to 48% of brexpiprazole exposure (AUC) in plasma. DM-3411 is considered not to contribute to the therapeutic effects of brexpiprazole.

Based on in vitro data, brexpiprazole showed little to no inhibition of CYP450 isozymes.

Excretion
Following a single oral dose of [14C]-labeled brexpiprazole, approximately 25% and 46% of the administered radioactivity was recovered in the urine and feces, respectively. Less than 1% of unchanged brexpiprazole was excreted in the urine, and approximately 14% of the oral dose was recovered unchanged in the feces. Apparent oral clearance of a brexpiprazole oral tablet after once daily administration is 19.8 (±11.4) mL/h/kg. After multiple once-daily administrations of brexpiprazole tablets, the terminal elimination half-lives of brexpiprazole and its major metabolite, DM-3411, were 91 hours and 86 hours, respectively.

Studies in Specific Populations
Exposure of brexpiprazole in specific populations are summarized in Figure 1. Population pharmacokinetic (PK) analysis indicated exposure of brexpiprazole in patients with moderate renal impairment was higher compared to patients with normal renal function.

Figure 1: Effect of Intrinsic Factors on Brexpiprazole Pharmacokinetics

Pediatric use information is approved for Otsuka Pharmaceutical Company, Ltd.’s Rexulti® (brexpiprazole) tablets. However, due to Otsuka Pharmaceutical Company, LTD.’s marketing exclusivity rights, this drug product is not labeled with that information.

Drug Interaction Studies

Effects of other drugs on the exposures of brexpiprazole are summarized in Figure 2. Based on simulation, a 5.1-fold increase in AUC values at steady-state is expected when extensive metabolizers of CYP2D6 are administered with both strong CYP2D6 and CYP3A4 inhibitors. A 4.8-fold increase in mean AUC values at steady-state is expected in poor metabolizers of CYP2D6 administered with strong CYP3A4 inhibitors [see Drug Interactions (7.1)].

Figure 2: The Effect of Other Drugs on Brexpiprazole Pharmacokinetics

The effects of brexpiprazole tablets on the exposures of other drugs are summarized in Figure 3.

Figure 3: The Effect of Brexpiprazole Tablets on Pharmacokinetics of Other Drugs

13 NONCLINICAL TOXICOLOGY

13.1 Carcinogenesis, Mutagenesis, Impairment of Fertility

Carcinogenesis

Lifetime carcinogenicity studies were conducted in ICR mice and Sprague Dawley rats. Brexpiprazole was administered orally for two years to male and female mice at doses of 0.75 mg/kg/day, 2 mg/kg/day, and 5 mg/kg/day (0.9 to 6.1 times the oral MRHD of 4 mg/day based on mg/m^2 body surface area) and to male and female rats at doses of 1 mg/kg, 3 mg/kg, and 10 mg/kg and 3 mg/kg/day, 10 mg/kg/day, and 30 mg/kg/day, respectively (2.4 to 24 and 7.3 to 73 times the oral MRHD, males and females). In female mice, the incidence of mammary gland adenocarcinoma was increased at all doses, and the incidence of adenosquamous carcinoma was increased at 2.4 and 6.1 times the MRHD. No increase in the incidence of tumors was observed in male mice. In the rat study, brexpiprazole was not carcinogenic in either sex at doses up to 73 times the MRHD.

Proliferative and/or neoplastic changes in the mammary and pituitary glands of rodents have been observed following chronic administration of antipsychotic drugs and are considered to be prolactin mediated. The potential for increasing serum prolactin level of brexpiprazole was shown in both mice and rats. The relevance for human risk of the findings of prolactin-mediated endocrine tumors in rodents is unknown.

Mutagenesis

Brexpiprazole was not mutagenic when tested in the in vitro bacterial reverse mutation assay (Ames test). Brexpiprazole was negative for clastogenic activity in the in vivo micronucleus assay in rats and was not genotoxic in the in vivo/in vitro unscheduled DNA synthesis assay in rats. In vitro with mammalian cells brexpiprazole was clastogenic but only at doses that induced cytotoxicity. Based on a weight of evidence, brexpiprazole is not considered to present a genotoxic risk to humans.

Impairment of Fertility

Female rats were treated with oral doses of 0.3 mg/kg/day, 3 mg/kg/day, or 30 mg/kg/day (0.7, 7.3, and 73 times the oral MRHD on a mg/m^2 basis) prior to mating with untreated males and continuing through conception and implantation. Estrus cycle irregularities and decreased fertility were observed at 3 mg/kg/day and 30 mg/kg/day. Prolonged duration of pairing and increased preimplantation losses were observed at 30 mg/kg/day.

Male rats were treated with oral doses of 3 mg/kg/day, 10 mg/kg/day, or 100 mg/kg/day (7.3, 24, and 240 times the oral MRHD on a mg/m^2 basis) for 63 days prior to mating with untreated females and throughout the 14 days of mating. No differences were observed in the duration of mating or fertility indices in males at any dose of brexpiprazole.

14 CLINICAL STUDIES

14.1 Adjunctive Treatment of Major Depressive Disorder

The efficacy of brexpiprazole tablets in the adjunctive treatment of major depressive disorder (MDD) was evaluated in two 6-week double-blind, placebo-controlled, fixed-dose trials of adult patients meeting DSM-IV-TR criteria for MDD, with or without symptoms of anxiety, who had an inadequate response to prior antidepressant therapy (1 to 3 courses) in the current episode and who had also demonstrated an inadequate response throughout the 8 weeks of prospective antidepressant treatment (with escitalopram, fluoxetine, paroxetine controlled-release, sertraline, duloxetine delayed release, or venlafaxine extended release). Inadequate response during the prospective antidepressant treatment phase was defined as having persistent symptoms without substantial improvement throughout the course of treatment.

Patients in Study 228 (hereafter “Study 1”) were randomized to brexpiprazole tablets 2 mg once a day or placebo. Patients in Study 227 (hereafter “Study 2”) were randomized to brexpiprazole tablets 1 mg or 3 mg once a day or placebo. For patients randomized to brexpiprazole tablets, all patients initiated treatment at 0.5 mg once daily during Week 1. At Week 2, the brexpiprazole tablets dosage was increased to 1 mg in all treatment groups, and either maintained at 1 mg or increased to 2 mg or 3 mg once daily, based on treatment assignment, from Week 3 onwards. The dosages were then maintained for the 4 remaining weeks.

The primary endpoint was change from baseline to Week 6 in the Montgomery-Asberg Depression Rating Scale (MADRS), a 10-item clinician-related scale used to assess the degree of depressive symptomatology, with 0 representing no symptoms and 60 representing worst symptoms.

At randomization, the mean MADRS total score was 27. In Studies 1 and 2, brexpiprazole tablets (plus ADT) 2 mg/day and 3 mg/day were superior to placebo plus ADT in reducing mean MADRS total scores. Results from the primary efficacy parameters for both fixed dose trials are shown below in Table 10. Figure 4 below shows the time course of response based on the primary efficacy measure (MADRS) in Study 1.

Table 10: Summary of Efficacy Results for Studies 1 and 2 for the Adjunctive Treatment of MDD
Study | Treatment Group | N | Primary Efficacy Measure: MADRS
Study | Treatment Group | N | Mean Baseline Score (SD) | LS Mean Change From Baseline (SE) | Placebo-Subtracted Differencea (95% CI)
1 | Brexpiprazole Tablets (2 mg/day) +ADT* Placebo +ADT | 175 178 | 26.9(5.7) 27.3(5.6) | -8.4(0.6) -5.2(0.6) | -3.2(-4.9,-1.5) --
2 | Brexpiprazole Tablets (1 mg/day) +ADT | 211 | 26.5(5.6) | -7.6(0.5) | -1.3 (-2.7,0.1)
2 | Brexpiprazole Tablets (3 mg/day) +ADT | 213 | 26.5(5.3) | -8.3(0.5) | -2.0(-3.4, -0.5)
2 | Placebo + ADT | 203 | 26.5(5.2) | -6.3(0.5) | --
SD: standard deviation; SE: standard error; LS Mean: least-squares mean; CI: unadjusted confidence interval
* Dosages statistically significantly superior to placebo
a Difference (drug minus placebo) in least-squares mean change from baseline

An examination of population subgroups did not suggest differential response based on age, gender, race or choice of prospective antidepressant.
Figure 4: Change from Baseline in MADRS Total Score by Study Visit (Week) in Patients with MDD in Adults (Study 1)

14.2 Schizophrenia

The efficacy of brexpiprazole tablets in the treatment of adults with schizophrenia was demonstrated in two 6-week randomized, double-blind, placebo-controlled, fixed-dose clinical trials in patients who met DSM-IV-TR criteria for schizophrenia.

In both studies, Study 231 (hereafter “Study 3”) and Study 230 (hereafter “Study 4”), patients were randomized to brexpiprazole tablets 2 or 4 mg once per day or placebo. Patients in the brexpiprazole tablets groups initiated treatment at 1 mg once daily on Days 1 to 4. The brexpiprazole tablets dosage was increased to 2 mg on Days 5 to 7. The dosage was then either maintained at 2 mg once daily or increased to 4 mg once daily, depending on treatment assignment, for the 5 remaining weeks.

The primary efficacy endpoint of both trials was the change from baseline to Week 6 in the Positive and Negative Syndrome Scale (PANSS) total score. The PANSS is a 30-item scale that measures positive symptoms of schizophrenia (7 items), negative symptoms of schizophrenia (7 items), and general psychopathology (16 items), each rated on a scale of 1 (absent) to 7 (extreme); the total PANSS scores range from 30 (best) to 210 (worst).

In Study 3, brexpiprazole tablets at both 2 mg/day and 4 mg/day was superior to placebo on the PANSS total score. In Study 4, brexpiprazole tablets 4 mg/day was superior to placebo on the PANSS total score (Table 11). Figure 5 shows the time course of response based on the primary efficacy measure (change from baseline in PANSS total score) in Study 3.

Examination of population subgroups based on age, gender and race did not suggest differential responsiveness

Table 11: Summary of Efficacy Results for Studies of Schizophrenia in Adults (Studies 3 and 4)
Study | Treatment Group | N | Primary Efficacy Measure: PANSS
Study | Treatment Group | N | Mean Baseline Score (SD) | LS Mean Change From Baseline (SE) | Placebo-Subtracted Differencea (95% CI)
3 | Brexpiprazole Tablets (2 mg/day)* | 180 | 95.9(13.8) | -20.7(1.5) | -8.7 (-13.1, -4.4)
3 | Brexpiprazole Tablets (4 mg/day)* | 178 | 94.7(12.1) | -19.7(1.5) | -7.6 (-12.0, -3.1)
3 | Placebo | 178 | 95.7(11.5) | -12.0(1.6) | --
4 | Brexpiprazole Tablets (2 mg/day) | 179 | 96.3(12.9) | -16.6(1.5) | -3.1(-7.2,1.1)
4 | Brexpiprazole Tablets (4 mg/day)* | 181 | 95.0(12.4) | -20.0(1.5) | -6.5(-10.6,-2.4)
4 | Placebo | 180 | 94.6(12.8) | -13.5(1.5) | --
SD: standard deviation; SE: standard error; LS Mean: least-squares mean; CI: unadjusted confidence interval
* Dosages statistically significantly superior to placebo
a Difference (drug minus placebo) in least-squares mean change from baseline

Figure 5: Change from Baseline in PANSS Total Score by Study Visit (Week) in Adult Patients with Schizophrenia (Study 3)

The safety and efficacy of brexpiprazole tablets as maintenance treatment in adults with schizophrenia aged 18 to 65 years were demonstrated in the maintenance phase of a randomized withdrawal trial (Study 331-10-232, hereafter “Study 5”). Patients were stabilized for at least 12 weeks on 1 mg/day to 4 mg/day of brexpiprazole tablets (N=202). They were then randomized in the double-blind treatment phase to either continue brexpiprazole tablets at their achieved stable dose (N=97), or to switch to placebo (N=105).

The primary endpoint in Study 5 was time from randomization to impending relapse during the double-blind phase, defined as: 1) Clinical Global Improvement score of greater than or equal to 5 (minimally worse) and an increase to a score greater than 4 on PANSS conceptual disorganization, hallucinatory behavior, suspiciousness, or unusual thought content items, with either a greater than or equal to 2 increase on a specific item or greater than or equal to 4 point increase on the combined four PANSS items, 2) hospitalization due to worsening of psychotic symptoms, 3) current suicidal behavior, or 4) violent/aggressive behavior.

A pre-specified interim analysis demonstrated a statistically significantly longer time to relapse in patients randomized to the brexpiprazole tablets group compared to placebo-treated patients. The trial was subsequently terminated early because maintenance of efficacy had been demonstrated. The Kaplan-Meier curves of the cumulative proportion of patients with relapse during the double-blind treatment phase for brexpiprazole tablets and placebo groups are shown in Figure 6. The key secondary endpoint, the proportion of patients who met the criteria for impending relapse, was statistically significantly lower in brexpiprazole tablets-treated patients compared with placebo group.

Figure 6: Kaplan-Meier Estimation of Percent Impending Relapse in Study 5

Note: A total of 202 patients were randomized. Among them, one placebo patient did not take investigational medicinal product and one brexpiprazole patient did not have post-randomization efficacy evaluations. These two patients were excluded from the efficacy analysis.

16 HOW SUPPLIED/STORAGE AND HANDLING

16.1 How Supplied

Brexpiprazole tablets have markings on both the side, and are available in the following strengths and package configurations (see below):

- 0.25 mg tablets are brown colored, round, biconvex, film-coated tablet, debossed with “BX” on one side and “6” on other side.
  NDC 27241-204-30 Bottles of 30
- 0.5 mg tablets are orange colored, round, biconvex, film-coated tablet, debossed with “BX” on one side and “5” on other side.
  NDC 27241-205-30 Bottles of 30
- 1 mg tablets are yellow colored, round, biconvex, film-coated tablet, debossed with “BX” on one side and “1” on other side.
  NDC 27241-206-30 Bottles of 30
- 2 mg tablets are light green to green colored, round, biconvex, film-coated tablet, debossed with “BX” on one side and “2” on other side.
  NDC 27241-207-30 Bottles of 30
- 3 mg tablets are pink colored, round, biconvex, film-coated tablet, debossed with “BX” on one side and “3” on other side.
  NDC 27241-208-30 Bottles of 30
- 4 mg tablets are white to off-white colored, round, biconvex, film-coated tablet, debossed with “BX” on one side and “4” on other side.
  NDC 27241-209-30 Bottles of 30

16.2 Storage

Store brexpiprazole tablets at 20°C t o 25°C (68°F to 77°F); excursions permitted to 15°C to 30°C (59°F to 86°F) [see USP Controlled Room Temperature].

17 PATIENT COUNSELING INFORMATION

Advise the patient or caregiver to read the FDA-approved patient labeling (Medication Guide).

Suicidal Thoughts and Behaviors

Advise patients and caregivers to look for the emergence of suicidality, especially early during treatment and when the dosage is adjusted up or down, and instruct them to report such symptoms to the healthcare provider [see Boxed Warning, Warnings and Precautions (5.2)].

Dosage and Administration

Advise patients that brexpiprazole tablets can be taken with or without food. Advise patients regarding importance of following dosage escalation instructions [see Dosage and Administration (2.1), (2.2)].

Neuroleptic Malignant Syndrome (NMS)

Counsel patients about a potentially fatal adverse reaction - neuroleptic malignant syndrome (NMS) - that has been reported in association with administration of antipsychotic drugs. Advise patients to contact a healthcare provider or report to the emergency room if they experience signs or symptoms of NMS [see Warnings and Precautions (5.4)].

Tardive Dyskinesia

Counsel patients on the signs and symptoms of tardive dyskinesia and to contact their healthcare provider if these abnormal movements occur [see Warnings and Precautions (5.5)].

Metabolic Changes

Educate patients about the risk of metabolic changes, how to recognize symptoms of hyperglycemia and diabetes mellitus, and the need for specific monitoring, including blood glucose, lipids, and weight [see Warnings and Precautions (5.6)].

Pathological Gambling and Other Compulsive Behaviors

Advise patients and their caregivers of the possibility that they may experience compulsive urges to shop, intense urges to gamble, compulsive sexual urges, binge eating and/or other compulsive urges and the inability to control these urges while taking brexpiprazole tablets. In some cases, but not all, the urges were reported to have stopped when the dose was reduced or stopped [see Warnings and Precautions (5.7)].

Leukopenia, Neutropenia and Agranulocytosis

Advise patients with a pre-existing low WBC or a history of drug-induced leukopenia/neutropenia that they should have their CBC monitored while taking brexpiprazole tablets [see Warnings and Precautions (5.8)].

Orthostatic Hypotension and Syncope

Educate patients about the risk of orthostatic hypotension and syncope, especially early in treatment, and also at times of reinitiating treatment or increases in dosage [see Warnings and Precautions (5.9)].

Heat Exposure and Dehydration

Counsel patients regarding appropriate care in avoiding overheating and dehydration [see Warnings and Precautions(5.12)].

Interference with Cognitive and Motor Performance

Caution patients about performing activities requiring mental alertness, such as operating hazardous machinery or operating a motor vehicle, until they are reasonably certain that brexpiprazole tablets therapy does not adversely affect their ability to engage in such activities [see Warnings and Precautions (5.14)].

Concomitant Medications

Advise patients to inform their healthcare providers of any changes to their current prescription or over-the-counter medications because there is a potential for clinically significant interactions [see Drug Interactions (7.1)].

Pregnancy

Advise patients that third trimester use of brexpiprazole tablets may cause extrapyramidal and/or withdrawal symptoms in a neonate and to notify their healthcare provider with a known or suspected pregnancy. Advise patients that there is a pregnancy exposure registry that monitors pregnancy outcomes in women exposed to brexpiprazole tablets during pregnancy [see Use in Specific Populations (8.1)].

Marketed by:
Ajanta Pharma USA Inc.
Bridgewater, NJ 08807.
Made in INDIA.

#All trademarks are the properties of their respective owners

Revised: 12/2022

MEDICATION GUIDE
Brexpiprazole (breks PIP ray zole)
Tablets

What is the most important information I should know about brexpiprazole tablets?
Brexpiprazole tablets may cause serious side effects, including:

- Increased risk of death in elderly people with dementia-related psychosis. Medicines like brexpiprazole tablets can raise the risk of death in elderly people who have lost touch with reality (psychosis) due to confusion and memory loss (dementia). Brexpiprazole tablets are not approved for the treatment of people with dementia-related psychosis.
- Increased risk of suicidal thoughts and actions. Antidepressant medicines may increase suicidal thoughts and actions in some children, adolescents, and young adults especially within the first few months of treatment or when the dose is changed.
  - Depression and other mental illnesses are the most important causes of suicidal thoughts and actions.

How can I watch for and try to prevent suicidal thoughts and actions in myself or a family member?

- Pay close attention to any changes, especially sudden changes in mood, behaviors, thoughts, or feelings. This is very important when brexpiprazole tablets or the antidepressant medicine is started or when the dose is changed.
- Call your healthcare provider right away to report new or sudden changes in mood, behavior, thoughts, or feelings, or if you develop suicidal thoughts or actions.
- Keep all follow-up visits with your healthcare provider as scheduled. Call your healthcare provider between visits as needed, especially if you have concerns about symptoms.

Call a healthcare provider right away if you or your family member have any of the following symptoms, especially if they are new, worse, or worry you:
o thoughts about suicide or dying o attempts to commit suicide
o new or worsening depression o new or worsening anxiety
o feeling very agitated or restless o panic attacks
o trouble sleeping (insomnia) o new or worsening irritability
o acting aggressive, being angry, or violent o acting on dangerous impulses
o an extreme increase in activity or talking (mania) o other unusual changes in behavior or mood

What are brexpiprazole tablets?
Brexpiprazole tablets are prescription medicine used:

- with other antidepressant medicines to treat major depressive disorder (MDD) in adults.
- to treat schizophrenia in adults

It is not known if brexpiprazole tablets are safe and effective in children with MDD.
It is not known if brexpiprazole tablets are safe and effective in children under 13 years of age with schizophrenia.
Do not take brexpiprazole tablets if you are allergic to brexpiprazole or any of the ingredients in brexpiprazole tablets. See the end of this Medication Guide for a complete list of ingredients in brexpiprazole tablets.

Before taking brexpiprazole tablets, tell your healthcare provider about all of your medical conditions, including if you:

- have or have had heart problems or a stroke
- have or have had low or high blood pressure
- have or have had diabetes or high blood sugar or a family history of diabetes or high blood sugar. Your healthcare provider should check your blood sugar before you start brexpiprazole tablets and during treatment with brexpiprazole tablets.
- have or have had high levels of total cholesterol, LDL cholesterol, or triglycerides, or low levels of HDL cholesterol
- have or have had seizures (convulsions)
- have or have had kidney or liver problems
- have or have had a low white blood cell count
- are pregnant or plan to become pregnant. Brexpiprazole tablets may harm your unborn baby. Taking brexpiprazole tablets during your third trimester of pregnancy may cause your baby to have abnormal muscle movements or withdrawal symptoms after birth.
  - Tell your healthcare provider if you become pregnant or think you are pregnant during treatment with brexpiprazole tablets.
  - If you become pregnant during treatment with brexpiprazole tablets, talk to your healthcare provider about registering with the National Pregnancy Registry for Atypical Antipsychotics. You can register by calling 1-866-961-2388 or visit http://womensmentalhealth.org/clinical-and-research-programs/pregnancyregistry/.
- are breastfeeding or plan to breastfeed. It is not known if brexpiprazole passes into your breast milk. Talk to your healthcare provider about the best way to feed your baby during treatment with brexpiprazole tablets.

Tell your healthcare provider about all the medicines you take, including prescription and over-the-counter medicines, vitamins, and herbal supplements.
Brexpiprazole tablets and other medicines may affect each other causing possible serious side effects. Brexpiprazole tablets may affect the way other medicines work, and other medicines may affect how brexpiprazole tablets works. Your healthcare provider can tell you if it is safe to take brexpiprazole tablets with your other medicines. Do not start or stop any medicines during treatment with brexpiprazole tablets without first talking to your healthcare provider.
Know the medicines you take. Keep a list of them to show your healthcare provider and pharmacist when you get a new medicine.

How should I take brexpiprazole tablets?

- Take brexpiprazole tablets exactly as your healthcare provider tells you to take it. Your healthcare provider may change your dose if needed. Do not change the dose or stop taking brexpiprazole tablets without first talking to your healthcare provider.
- Take brexpiprazole tablets 1 time each day with or without food.
- If you take too much brexpiprazole tablets, call your healthcare provider or a certified Poison Control Center at 1-800-222-1222 or go to www.poison.org, or go to the nearest hospital emergency room right away.

What should I avoid while taking brexpiprazole tablets?

- Do not drive a car, operate machinery, or do other dangerous activities until you know how brexpiprazole tablets affects you. Brexpiprazole tablets may make you feel drowsy.
- Do not become too hot or dehydrated during treatment with brexpiprazole tablets
  - Do not exercise too much.
  - In hot weather, stay inside in a cool place if possible.
  - Stay out of the sun.
  - Do not wear too much clothing or heavy clothing.
  - Drink plenty of water

What are the possible side effects of brexpiprazole tablets?
Brexpiprazole tablets may cause serious side effects, including:

- See “What is the most important information I should know about brexpiprazole tablets?”
- Stroke (cerebrovascular problems) in elderly people with dementia-related psychosis that can lead to death.
- Neuroleptic Malignant Syndrome (NMS) is a serious condition that can lead to death: Call your healthcare provider or go to the nearest hospital emergency room right away if you have some or all of the following signs and symptoms of NMS:
- high fever
- changes in your breathing, heart rate, and blood pressure.
- stiff muscles
- confusion
- increased sweating

- Uncontrolled body movements (tardive dyskinesia): Brexpiprazole tablets may cause movements that you cannot control in your face, tongue, or other body parts. Tardive dyskinesia may not go away, even if you stop taking brexpiprazole tablets. Tardive dyskinesia may also start after you stop taking brexpiprazole tablets.
- Problems with your metabolism such as:
  - high blood sugar (hyperglycemia) and diabetes. Increases in blood sugar can happen in some people who take brexpiprazole tablets. Extremely high blood sugar can lead to coma or death. Your healthcare provider should check your blood sugar before you start, or soon after you start brexpiprazole tablets and then regularly during long term treatment with brexpiprazole tablets.

Call your healthcare provider if you have any of these symptoms of high blood sugar during treatment with brexpiprazole tablets:

- feel very thirsty
  feel very hungry
- feel sick to your stomach
- feel weak or tired
- need to urinate more than usual
  feel confused, or your breath smells fruity

- increased fat levels (cholesterol and triglycerides) in your blood. Your healthcare provider should check the fat levels in your blood before you start, or soon after you start brexpiprazole tablets, and then periodically during treatment with brexpiprazole tablets.
- weight gain. You and your healthcare provider should check your weight before you start and often during treatment with brexpiprazole tablets.
- Unusual and uncontrollable (compulsive) urges. Some people taking brexpiprazole tablets have had strong unusual urges, to gamble and gambling that cannot be controlled (compulsive gambling). Other compulsive urges include sexual urges, shopping, and eating or binge eating. If you or your family members notice that you are having unusual strong urges, talk to your healthcare provider.
- Low white blood cell count. Your healthcare provider may do blood tests during the first few months of treatment with brexpiprazole tablets.
- Decreased blood pressure (orthostatic hypotension). You may feel lightheaded or faint when you rise too quickly from a sitting or lying position.
- Falls. Brexpiprazole tablets may make you sleepy or dizzy, may cause a decrease in your blood pressure when changing position (orthostatic hypotension), and can slow your thinking and motor skills which may lead to falls that can cause fractures or other injuries.
- Seizures (convulsions)
- Problems controlling your body temperature so that you feel too warm. See “What should I avoid while taking brexpiprazole tablets?”
- Difficulty swallowing that can cause food or liquid to get into your lungs
- Sleepiness, drowsiness, feeling tired, difficulty thinking and doing normal activities. See “What should I avoid while taking brexpiprazole tablets?”

The most common side effects of brexpiprazole tablets include weight gain and restlessness or feeling like you need to move (akathisia).
These are not all the possible side effects of brexpiprazole tablets.
Call your doctor for medical advice about side effects. You may report side effects to FDA at 1-800-FDA-1088.

How should I store brexpiprazole tablets?
Store brexpiprazole tablets at room temperature, between 68°F to 77°F (20°C to 25°C).
Keep brexpiprazole tablets and all medicines out of the reach of children.

General information about the safe and effective use of brexpiprazole tablets.
Medicines are sometimes prescribed for purposes other than those listed in a Medication Guide. Do not use brexpiprazole tablets for a condition for which it was not prescribed. Do not give brexpiprazole tablets to other people, even if they have the same symptoms you have. It may harm them. You can ask your pharmacist or healthcare provider for information about brexpiprazole tablets that is written for healthcare professionals.

What are the ingredients in brexpiprazole tablets?
Active ingredient: brexpiprazole
Inactive ingredients: microcrystalline cellulose, lactose monohydrate, low-substituted hydroxypropyl cellulose, hydroxypropyl cellulose, magnesium stearate, hypromellose, talc, propylene glycol, polyethylene glycol. Colorants includes titanium dioxide, iron oxide red (0.25 mg and 3 mg), FD&C Yellow #6 (0.5 mg), iron oxide yellow (1 mg, 2 mg and 3 mg), FD&C Blue #2 (2 mg). Pediatric use information is approved for Otsuka Pharmaceutical Company, Ltd.’s Rexulti® (brexpiprazole) tablets. However, due to Otsuka Pharmaceutical Company, LTD.’s marketing exclusivity rights, this drug product is not labeled with that information.
Marketed by:
Ajanta Pharma USA Inc.
Bridgewater, NJ 08807.
Made in INDIA.
#All trademarks are the properties of their respective owners

This Medication Guide has been approved by the U.S. Food and Drug Administration

Revised: 12/2022

PACKAGE LABEL.PRINCIPAL DISPLAY PANEL

NDC 27241-204-30
0.25 mg
30 Tablets
Brexpiprazole Tablets
PHARMACIST: DISPENSE THE ACCOMPANYNG MEDICATION GUIDE TO EACH PATIENT
Rx Only
ajanta

NDC 27241-205-30
0.5 mg
30 Tablets
Brexpiprazole Tablets
PHARMACIST: DISPENSE THE ACCOMPANYNG MEDICATION GUIDE TO EACH PATIENT
Rx Only
ajanta

NDC 27241-206-30
1 mg
30 Tablets
Brexpiprazole Tablets
PHARMACIST: DISPENSE THE ACCOMPANYNG MEDICATION GUIDE TO EACH PATIENT
Rx Only
ajanta

NDC 27241-207-30
2 mg
30 Tablets
Brexpiprazole Tablets
PHARMACIST: DISPENSE THE ACCOMPANYNG MEDICATION GUIDE TO EACH PATIENT
Rx Only
ajanta

NDC 27241-208-30
3 mg
30 Tablets
Brexpiprazole Tablets
PHARMACIST: DISPENSE THE ACCOMPANYNG MEDICATION GUIDE TO EACH PATIENT
Rx Only
ajanta

NDC 27241-209-30
4 mg
30 Tablets
Brexpiprazole Tablets
PHARMACIST: DISPENSE THE ACCOMPANYNG MEDICATION GUIDE TO EACH PATIENT
Rx Only
ajanta